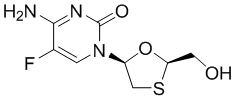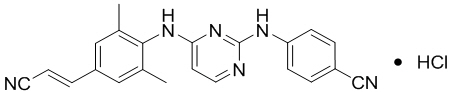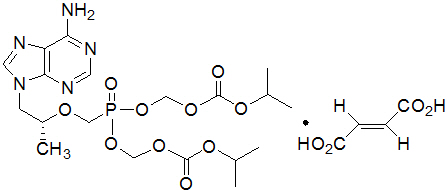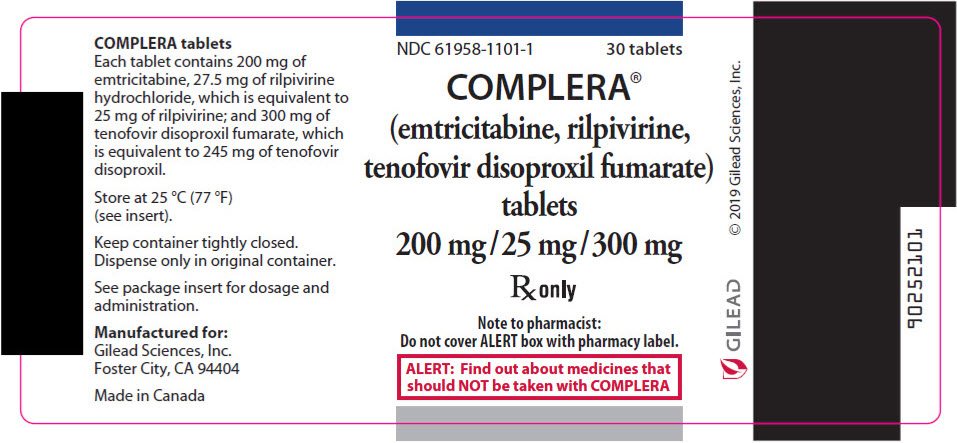 DRUG LABEL: COMPLERA
NDC: 61958-1101 | Form: TABLET, FILM COATED
Manufacturer: Gilead Sciences, Inc.
Category: prescription | Type: HUMAN PRESCRIPTION DRUG LABEL
Date: 20250716

ACTIVE INGREDIENTS: emtricitabine 200 mg/1 1; rilpivirine hydrochloride 25 mg/1 1; tenofovir disoproxil fumarate 300 mg/1 1
INACTIVE INGREDIENTS: microcrystalline cellulose; lactose monohydrate; Povidone, Unspecified; polysorbate 20; croscarmellose sodium; magnesium stearate; starch, corn; hypromellose, unspecified; FD&C Blue No. 2; aluminum oxide; polyethylene glycol, unspecified; ferric oxide red; titanium dioxide; triacetin; FD&C Yellow No. 6; water

HIGHLIGHTS OF PRESCRIBING INFORMATION

These highlights do not include all the information needed to use COMPLERA safely and effectively. See full prescribing information for COMPLERA.
COMPLERA® (emtricitabine, rilpivirine, tenofovir disoproxil fumarate) tablets, for oral use
Initial U.S. Approval: 2011

WARNING: POSTTREATMENT ACUTE EXACERBATION OF HEPATITIS B

See full prescribing information for complete boxed warning.

Severe acute exacerbations of hepatitis B virus (HBV) have been reported in patients coinfected with HIV-1 and HBV who have discontinued products containing emtricitabine (FTC) and/or tenofovir disoproxil fumarate (TDF), two of the components of COMPLERA. Closely monitor hepatic function with both clinical and laboratory follow-up for at least several months in patients who are coinfected with HIV-1 and HBV and discontinue COMPLERA. If appropriate, initiation of anti-hepatitis B therapy may be warranted. (5.1)

RECENT MAJOR CHANGES

Warnings and Precautions
Immune Reconstitution Syndrome (5.9) | 11/2019

1 INDICATIONS AND USAGE

COMPLERA, a combination of two nucleoside analog HIV-1 reverse transcriptase inhibitors (emtricitabine and tenofovir disoproxil fumarate) and one non-nucleoside reverse transcriptase inhibitor (rilpivirine), is indicated for use as a complete regimen for the treatment of HIV-1 infection in patients weighing at least 35 kg (1) as initial therapy in those with no antiretroviral treatment history and with HIV-1 RNA less than or equal to 100,000 copies/mL at the start of therapy, or (2) or to replace a stable antiretroviral regiment in those who are virologically suppressed (HIV-1 RNA <50 copies/mL) on a stable antiretroviral regimen for at least 6 months with no treatment failure and no known substitutions associated with resistance to the individual components of COMPLERA. (1, 14)

Limitations of Use:

- More rilpivirine-treated subjects with HIV-1 RNA greater than 100,000 copies/mL at the start of therapy experienced virologic failure (HIV-1 RNA ≥50 copies/mL) compared to rilpivirine-treated subjects with HIV-1 RNA less than or equal to 100,000 copies/mL. (1, 14)

2 DOSAGE AND ADMINISTRATION

- Testing: Prior to or when initiating COMPLERA, test for hepatitis B virus infection. Prior to initiation and during treatment with COMPLERA, on a clinically appropriate schedule, assess serum creatinine, estimated creatinine clearance, urine glucose, and urine protein in all patients. In patients with chronic kidney disease, also assess serum phosphorus. (2.1)
- Recommended dosage in adults and pediatric patients weighing at least 35 kg: One tablet taken orally once daily with food. (2.2)
- For pregnant patients who are already on COMPLERA prior to pregnancy and who are virologically suppressed (HIV-1 RNA less than 50 copies per mL), one tablet taken once daily may be continued. Lower exposures of rilpivirine were observed during pregnancy; therefore, viral load should be monitored closely. (2.3)
- Renal impairment: Not recommended in patients with estimated creatinine clearance below 50 mL per minute. (2.4)
- Recommended dosage with rifabutin coadministration: an additional 25 mg tablet of rilpivirine (Edurant) once per day taken concomitantly with COMPLERA and with a meal for the duration of the rifabutin coadministration. (2.5, 7.6, 12.3)

3 DOSAGE FORMS AND STRENGTHS

Tablets: 200 mg of emtricitabine, 25 mg of rilpivirine, and 300 mg of tenofovir disoproxil fumarate. (3)

4 CONTRAINDICATIONS

COMPLERA is contraindicated when coadministered with drugs which may result in loss of virologic response and possible resistance to COMPLERA. (4)

5 WARNINGS AND PRECAUTIONS

- Skin and Hypersensitivity Reactions: Severe skin and hypersensitivity reactions have been reported during postmarketing experience, including cases of Drug Reaction with Eosinophilia and Systemic Symptoms (DRESS). Immediately discontinue treatment if hypersensitivity or rash with systemic symptoms or elevations in hepatic serum biochemistries develops and closely monitor clinical status, including hepatic serum biochemistries. (5.2)
- Hepatotoxicity: Hepatic adverse events have been reported in patients receiving a rilpivirine-containing regimen. Monitor liver-associated tests before and during treatment with COMPLERA in patients with underlying hepatic disease or marked elevations in liver-associated tests. Also consider monitoring liver-associated tests in patients without risk factors. (5.3)
- Depressive disorders: Severe depressive disorders have been reported. Immediate medical evaluation is recommended for severe depressive disorders. (5.4)
- New onset or worsening renal impairment: Can include acute renal failure and Fanconi syndrome. Avoid administering COMPLERA with concurrent or recent use of nephrotoxic drugs. (5.5)
- Decreases in bone mineral density (BMD): Consider monitoring BMD in patients with a history of pathologic fracture or other risk factors of osteoporosis or bone loss. (5.6)
- Concomitant use of COMPLERA with drugs with a known risk to prolong the QTc interval of the electrocardiogram may increase the risk of Torsade de Pointes. (5.7)
- Lactic acidosis/severe hepatomegaly with steatosis: Discontinue treatment in patients who develop symptoms or laboratory findings suggestive of lactic acidosis or pronounced hepatotoxicity. (5.8)
- Immune reconstitution syndrome: May necessitate further evaluation and treatment. (5.9)

6 ADVERSE REACTIONS

- Most common adverse reactions to rilpivirine (incidence greater than or equal to 2%, Grades 2–4) are depressive disorders, insomnia, and headache. (6.1)
- Most common adverse reactions to emtricitabine and tenofovir disoproxil fumarate (incidence greater than or equal to 10%) are diarrhea, nausea, fatigue, headache, dizziness, depression, insomnia, abnormal dreams, and rash. (6.1)

To report SUSPECTED ADVERSE REACTIONS, contact Gilead Sciences, Inc. at 1-800-GILEAD-5 or FDA at 1-800-FDA-1088 or www.fda.gov/medwatch

7 DRUG INTERACTIONS

- COMPLERA is a complete regimen for the treatment of HIV-1 infection; therefore, coadministration with other antiretroviral medications for treatment of HIV-1 infection is not recommended. (7.1)
- Consult the Full Prescribing Information prior to and during treatment for important drug interactions. (4, 5.7, 7)

8 USE IN SPECIFIC POPULATIONS

- Pregnancy: Monitor viral load closely during pregnancy as rilpivirine exposures were generally lower during pregnancy. (2.3, 8.1, 12.3)
- Lactation: Breastfeeding not recommended due to the potential for HIV-1 transmission. (8.2)
- Pediatrics: Not recommended for patients weighing less than 35 kg. (8.4)

FULL PRESCRIBING INFORMATION

WARNING: POSTTREATMENT ACUTE EXACERBATION OF HEPATITIS B

Severe acute exacerbations of hepatitis B virus (HBV) have been reported in patients who are coinfected with HBV and HIV-1 and have discontinued products containing emtricitabine (FTC) and/or tenofovir disoproxil fumarate (TDF), two of the components of COMPLERA.

Closely monitor hepatic function with both clinical and laboratory follow-up for at least several months in patients who are coinfected with HIV-1 and HBV and discontinue COMPLERA. If appropriate, initiation of anti-hepatitis B therapy may be warranted [see Warnings and Precautions (5.1)].

1 INDICATIONS AND USAGE

COMPLERA® is indicated as a complete regimen for the treatment of HIV-1 infection in adults and pediatric patients weighing at least 35 kg:

- as initial therapy in those with no antiretroviral treatment history with HIV-1 RNA less than or equal to 100,000 copies/mL at the start of therapy or
- to replace a stable antiretroviral regimen in those who are virologically suppressed (HIV-1 RNA less than 50 copies/mL) on a stable antiretroviral regimen for at least 6 months with no treatment failure and no known substitutions associated with resistance to the individual components of COMPLERA [see Microbiology (12.4) and Clinical Studies (14)].

Limitations of Use:

- More rilpivirine-treated subjects with HIV-1 RNA greater than 100,000 copies/mL at the start of therapy experienced virologic failure (HIV-1 RNA ≥50 copies/mL) compared to rilpivirine-treated subjects with HIV-1 RNA less than or equal to 100,000 copies/mL [see Clinical Studies (14)].

2 DOSAGE AND ADMINISTRATION

2.1 Testing Prior to Initiation and During Treatment with COMPLERA

Prior to or when initiating COMPLERA, test patients for hepatitis B virus infection [see Warnings and Precautions (5.1)].

Prior to initiation of COMPLERA, and during treatment with COMPLERA, on a clinically appropriate schedule, assess serum creatinine, estimated creatinine clearance, urine glucose and urine protein in all patients. In patients with chronic kidney disease, also assess serum phosphorus [see Warnings and Precautions (5.5)].

2.2 Recommended Dosage

COMPLERA is a three-drug fixed dose combination product containing 200 mg of emtricitabine (FTC), 25 mg of rilpivirine (RPV), and 300 mg of tenofovir disoproxil fumarate (TDF). The recommended dosage of COMPLERA in adult and pediatric patients weighing at least 35 kg is one tablet taken orally once daily with food [see Use in Specific Populations (8.4) and Clinical Pharmacology (12.3)].

2.3 Recommended Dosage During Pregnancy

For pregnant patients who are already on COMPLERA prior to pregnancy and are virologically suppressed (HIV-1 RNA less than 50 copies per mL), one tablet of COMPLERA taken once daily may be continued. Lower exposures of rilpivirine, a component of COMPLERA, were observed during pregnancy, therefore viral load should be monitored closely [see Use in Specific Populations (8.1) and Clinical Pharmacology (12.3)].

2.4 Not Recommended in Patients with Moderate or Severe Renal Impairment

COMPLERA is not recommended in patients with moderate or severe renal impairment (estimated creatinine clearance below 50 mL per minute) [see Warnings and Precautions (5.5) and Use in Specific Populations (8.6)].

2.5 Recommended Dosage with Rifabutin Coadministration

If COMPLERA is coadministered with rifabutin, take an additional 25 mg tablet of rilpivirine (Edurant®) with COMPLERA once daily with a meal for the duration of the rifabutin coadministration [see Drug Interactions (7.6) and Clinical Pharmacology (12.3)].

3 DOSAGE FORMS AND STRENGTHS

Each COMPLERA tablet contains 200 mg of emtricitabine (FTC), 27.5 mg of rilpivirine hydrochloride (equivalent to 25 mg of rilpivirine [RPV]), and 300 mg of tenofovir disoproxil fumarate (TDF, equivalent to 245 mg of tenofovir disoproxil).

The tablets are purplish pink, capsule shaped, film coated, debossed with "GSI" on one side, and plain faced on the other side.

4 CONTRAINDICATIONS

COMPLERA is contraindicated when coadministered with the following drugs; coadministration may result in loss of virologic response and possible resistance to COMPLERA or to the class of NNRTIs [see Warnings and Precautions (5.7), Drug Interactions (7), and Clinical Pharmacology (12.3)]:

- Anticonvulsants: carbamazepine, oxcarbazepine, phenobarbital, phenytoin
- Antimycobacterials: rifampin, rifapentine
- Glucocorticoid (systemic): dexamethasone (more than a single-dose)
- Herbal Products: St John's wort (Hypericum perforatum)
- Proton Pump Inhibitors: e.g., dexlansoprazole, esomeprazole, lansoprazole, omeprazole, pantoprazole, rabeprazole

5 WARNINGS AND PRECAUTIONS

5.1 Severe Acute Exacerbation of Hepatitis B in Patients Coinfected with HIV-1 and HBV

Test all patients with HIV-1 for the presence of chronic hepatitis B virus (HBV) before or when initiating antiretroviral therapy [see Dosage and Administration (2.1)].

Severe acute exacerbations of hepatitis B (e.g., liver decompensation and liver failure) have been reported in patients who are coinfected with HBV and HIV-1 and have discontinued products containing FTC and/or TDF, two of the components of COMPLERA. Patients coinfected with HIV-1 and HBV who discontinue COMPLERA should be closely monitored with both clinical and laboratory follow-up for at least several months after stopping treatment with COMPLERA. If appropriate, initiation of anti-hepatitis B therapy may be warranted, especially in patients with advanced liver disease or cirrhosis, since posttreatment exacerbation of hepatitis may lead to hepatic decompensation and liver failure.

5.2 Skin and Hypersensitivity Reactions

Severe skin and hypersensitivity reactions have been reported during the postmarketing experience, including cases of Drug Reaction with Eosinophilia and Systemic Symptoms (DRESS) with RPV-containing regimens. While some skin reactions were accompanied by constitutional symptoms such as fever, other skin reactions were associated with organ dysfunctions, including elevations in hepatic serum biochemistries. During the Phase 3 clinical trials, treatment-related rashes with at least Grade 2 severity were reported in 1% of subjects receiving RPV plus FTC/TDF. Overall, most rashes were Grade 1 or 2 and occurred in the first four to six weeks of therapy [see Adverse Reactions (6.1 and 6.2)].

Discontinue COMPLERA immediately if signs or symptoms of severe skin or hypersensitivity reactions develop, including but not limited to, severe rash or rash accompanied by fever, blisters, mucosal involvement, conjunctivitis, facial edema, angioedema, hepatitis, or eosinophilia. Clinical status including laboratory parameters should be monitored and appropriate therapy should be initiated.

5.3 Hepatotoxicity

Hepatic adverse events have been reported in patients receiving an RPV-containing regimen. Patients with underlying hepatitis B or C virus infection, or marked elevations in liver-associated tests prior to treatment, may be at increased risk for worsening or development of liver-associated test elevations with use of COMPLERA. A few cases of hepatic toxicity have been reported in adult patients receiving an RPV-containing regimen who had no pre-existing hepatic disease or other identifiable risk factors. Appropriate laboratory testing prior to initiating therapy and monitoring for hepatotoxicity during therapy with COMPLERA is recommended in patients with underlying hepatic disease such as hepatitis B or C, or in patients with marked elevations in liver-associated tests prior to treatment initiation. Liver-associated test monitoring should also be considered for patients without pre-existing hepatic dysfunction or other risk factors.

5.4 Depressive Disorders

The adverse reaction depressive disorders (depressed mood, depression, dysphoria, major depression, mood altered, negative thoughts, suicide attempt, suicidal ideation) has been reported with RPV. Patients with severe depressive symptoms should seek immediate medical evaluation to assess the possibility that the symptoms are related to COMPLERA, and if so, to determine whether the risks of continued therapy outweigh the benefits.

During the Phase 3 trials in adults (N=1368) through 96 weeks, the incidence of depressive disorders (regardless of causality, severity) reported among RPV (n=686) or efavirenz (EFV, n=682) was 9% and 8%, respectively. Most events were mild or moderate in severity. The incidence of Grades 3 and 4 depressive disorders (regardless of causality) was 1% for both RPV and EFV. The incidence of discontinuation due to depressive disorders among RPV or EFV was 1% in each arm. Suicidal ideation was reported in 4 subjects in each arm while suicide attempt was reported in 2 subjects in the RPV arm.

During the Phase 2 trial in pediatric subjects 12 to less than 18 years of age (N=36) receiving RPV through 48 weeks, the incidence of depressive disorders (regardless of causality, severity) was 19.4% (7/36). Most events were mild or moderate in severity. The incidence of Grade 3 and 4 depressive disorders (regardless of causality) was 5.6% (2/36). None of the subjects discontinued due to depressive disorders. Suicidal ideation and suicide attempt were reported in 1 subject.

5.5 New Onset or Worsening Renal Impairment

Renal impairment, including cases of acute renal failure and Fanconi syndrome (renal tubular injury with severe hypophosphatemia), has been reported with the use of TDF [see Adverse Reactions (6.2)].

Prior to initiation of COMPLERA, and during treatment with COMPLERA, on a clinically appropriate schedule, assess serum creatinine, estimated creatinine clearance, urine glucose, and urine protein in all patients. In patients with chronic kidney disease, also assess serum phosphorus.

COMPLERA should be avoided with concurrent or recent use of a nephrotoxic agent (e.g., high-dose or multiple nonsteroidal anti-inflammatory drugs [NSAIDs]) [see Drug Interactions (7.4)]. Cases of acute renal failure after initiation of high-dose or multiple NSAIDs have been reported in HIV-infected patients with risk factors for renal dysfunction who appeared stable on TDF. Some patients required hospitalization and renal replacement therapy. Alternatives to NSAIDs should be considered, if needed, in patients at risk for renal dysfunction.

Persistent or worsening bone pain, pain in extremities, fractures, and/or muscular pain or weakness may be manifestations of proximal renal tubulopathy and should prompt an evaluation of renal function in at-risk patients.

Emtricitabine and TDF are principally eliminated by the kidney; however, RPV is not. Since COMPLERA is a combination product and the dose of the individual components cannot be altered, COMPLERA is not recommended in patients with estimated creatinine clearance below 50 mL per minute [see Use in Specific Populations (8.6)].

5.6 Bone Loss and Mineralization Defects

Bone Mineral Density

In clinical trials in HIV-1-infected adults, TDF, a component of COMPLERA, was associated with slightly greater decreases in bone mineral density (BMD) and increases in biochemical markers of bone metabolism, suggesting increased bone turnover relative to comparators. Serum parathyroid hormone levels and 1,25 Vitamin D levels were also higher in subjects receiving TDF.

Clinical trials evaluating TDF in pediatric and adolescent subjects were conducted. Under normal circumstances, BMD increases rapidly in pediatric patients. In HIV-1-infected subjects aged 2 years to less than 18 years, bone effects were similar to those observed in adult subjects and suggest increased bone turnover. Total body BMD gain was less in the TDF-treated HIV-1-infected pediatric subjects as compared to the control groups. Similar trends were observed in chronic hepatitis B-infected adolescent subjects aged 12 years to less than 18 years. In all pediatric trials, skeletal growth (height) appeared to be unaffected.

The effects of TDF-associated changes in BMD and biochemical markers on long-term bone health and future fracture risk are unknown. Assessment of BMD should be considered for adult and pediatric patients who have a history of pathologic bone fracture or other risk factors for osteoporosis or bone loss. Although the effect of supplementation with calcium and Vitamin D was not studied, such supplementation may be beneficial for all patients. If bone abnormalities are suspected, then appropriate consultation should be obtained.

Mineralization Defects

Cases of osteomalacia associated with proximal renal tubulopathy, manifested as bone pain or pain in extremities and which may contribute to fractures, have been reported in association with the use of TDF [see Adverse Reactions (6.2)]. Arthralgias and muscle pain or weakness have also been reported in cases of proximal renal tubulopathy. Hypophosphatemia and osteomalacia secondary to proximal renal tubulopathy should be considered in patients at risk of renal dysfunction who present with persistent or worsening bone or muscle symptoms while receiving products containing TDF [See Warnings and Precautions (5.5)].

5.7 Risk of Adverse Reactions or Loss of Virologic Response Due to Drug Interactions

The concomitant use of COMPLERA and other drugs may result in potentially significant drug interactions, some of which may lead to [see Dosage and Administration (2.5), Contraindications (4), and Drug Interactions (7)]:

- Loss of therapeutic effect of COMPLERA and possible development of resistance due to reduced exposure to RPV.
- Possible clinically significant adverse reaction from greater exposures of components of COMPLERA.

In healthy subjects, 75 mg once daily and 300 mg once daily doses of RPV (3 times and 12 times the dose in COMPLERA) have been shown to prolong the QTc interval of the electrocardiogram. Consider alternatives to COMPLERA when coadministered with a drug that is known to have a risk of Torsade de Pointes [see Drug Interactions (7) and Clinical Pharmacology (12.2)].

See Table 4 for steps to prevent or manage these possible and known significant drug interactions, including dosing recommendations. Consider the potential for drug interactions prior to and during COMPLERA therapy and review concomitant medications during COMPLERA therapy.

5.8 Lactic Acidosis/Severe Hepatomegaly with Steatosis

Lactic acidosis and severe hepatomegaly with steatosis, including fatal cases, have been reported with the use of nucleoside analogs, including TDF and FTC, components of COMPLERA, alone or in combination with other antiretrovirals. Treatment with COMPLERA should be suspended in any patient who develops clinical or laboratory findings suggestive of lactic acidosis or pronounced hepatotoxicity (which may include hepatomegaly and steatosis even in the absence of marked transaminase elevations).

5.9 Immune Reconstitution Syndrome

Immune reconstitution syndrome has been reported in patients treated with combination antiretroviral therapy, including the components of COMPLERA. During the initial phase of combination antiretroviral treatment, patients whose immune system responds may develop an inflammatory response to indolent or residual opportunistic infections (such as Mycobacterium avium infection, cytomegalovirus, Pneumocystis jirovecii pneumonia [PCP], or tuberculosis), which may necessitate further evaluation and treatment.

Autoimmune disorders (such as Graves' disease, polymyositis, Guillain-Barré syndrome, and autoimmune hepatitis) have also been reported to occur in the setting of immune reconstitution; however, the time to onset is more variable and can occur many months after initiation of treatment.

6 ADVERSE REACTIONS

The following adverse reactions are discussed in other sections of the labeling:

- Severe Acute Exacerbations of Hepatitis B in Patients Coinfected with HIV-1 and HBV[see Warnings and Precautions (5.1)].
- Skin and Hypersensitivity Reactions [see Warnings and Precautions (5.2)].
- Hepatotoxicity [see Warnings and Precautions (5.3)].
- Depressive Disorders [see Warnings and Precautions (5.4)].
- New Onset or Worsening Renal Impairment [see Warnings and Precautions (5.5)].
- Bone Loss and Mineralization Defects [see Warnings and Precautions (5.6)].
- Lactic Acidosis/Severe Hepatomegaly with Steatosis [see Warnings and Precautions (5.8)].
- Immune Reconstitution Syndrome [see Warnings and Precautions (5.9)].

6.1 Clinical Trials Experience

Because clinical trials are conducted under widely varying conditions, adverse reaction rates observed in the clinical trials of a drug cannot be directly compared to rates in the clinical trials of another drug and may not reflect the rates observed in practice.

Adverse Reactions from Clinical Trials Experience in Adult Subjects

In HIV-1-Infected Adult Subjects With No Antiretroviral Treatment History

Studies C209 and C215

The safety assessment of RPV, used in combination with other antiretroviral drugs, is based on the Week 96 pooled data from 1368 subjects in the Phase 3 trials TMC278-C209 (ECHO) and TMC278-C215 (THRIVE) in antiretroviral treatment-naïve HIV-1-infected adult subjects. A total of 686 subjects received RPV in combination with other antiretroviral drugs as background regimen; most (N=550) received FTC/TDF as background regimen. The number of subjects randomized to the control arm EFV was 682, of which 546 received FTC/TDF as background regimen [see Clinical Studies (14)]. The median duration of exposure for subjects in either treatment arm was 104 weeks.

Adverse reactions observed at Week 96 in subjects who received RPV or EFV + FTC/TDF as background regimen are shown in Table 1. No new types of adverse reactions were identified between Week 48 and Week 96. The adverse reactions observed in this subset of subjects were generally consistent with those seen for the overall patient population participating in these studies (refer to the prescribing information for Edurant).

The proportion of subjects who discontinued treatment with RPV or EFV + FTC/TDF due to adverse reactions, regardless of severity, was 2% and 5%, respectively. The most common adverse reactions leading to discontinuation were psychiatric disorders: 9 (1.6%) subjects in the RPV + FTC/TDF arm and 12 (2.2%) subjects in the EFV + FTC/TDF arm. Rash led to discontinuation in 1 (0.2%) subject in the RPV + FTC/TDF arm and 10 (1.8%) subjects in the EFV + FTC/TDF arm.

Common Adverse Reactions: Clinical adverse reactions to RPV or EFV of at least moderate intensity (≥Grade 2) reported in at least 2% of adult subjects are shown in Table 1.

Table 1 Selected Adverse Reactions [Frequencies of adverse reactions are based on all Grades 2–4 treatment-emergent adverse events assessed to be related to study drug.] (Grades 2–4) Reported in ≥2% of Adult Subjects Receiving RPV or EFV in Combination with FTC/TDF in Studies C209 and C215 (Week 96 Analysis)
Preferred Term | RPV + FTC/TDF | EFV + FTC/TDF
Preferred Term | N=550 | N=546
Depressive disorders [Includes adverse reactions reported as depressed mood, depression, dysphoria, major depression, mood altered, negative thoughts, suicide attempt, suicide ideation.] | 2% | 2%
Headache | 2% | 2%
Insomnia | 2% | 2%
Abnormal dreams | 1% | 3%
Dizziness | 1% | 7%
Nausea | 1% | 2%
Rash | 1% | 5%

Rilpivirine: Adverse reactions of at least moderate intensity (≥Grade 2) that occurred in less than 2% of subjects treated with RPV plus any of the allowed background regimens (N=686) in clinical studies C209 and C215 include (grouped by Body System): vomiting, diarrhea, abdominal discomfort, abdominal pain, fatigue, cholecystitis, cholelithiasis, decreased appetite, somnolence, sleep disorders, anxiety, glomerulonephritis membranous, glomerulonephritis mesangioproliferative, and nephrolithiasis.

In Virologically Suppressed HIV-1-Infected Adult Subjects

No new adverse reactions to COMPLERA were identified in stable, virologically suppressed subjects switching to COMPLERA from a regimen containing a ritonavir-boosted protease inhibitor; however, the frequency of adverse reactions increased by 20% (Study 106) after switching to COMPLERA.

Emtricitabine and Tenofovir DF: The most common adverse reactions that occurred in at least 10% of HIV-1-infected treatment-naïve adult subjects in a Phase 3 clinical trial of FTC and TDF in combination with another antiretroviral agent were diarrhea, nausea, fatigue, headache, dizziness, depression, insomnia, abnormal dreams, and rash. Adverse reactions that occurred in at least 5% of treatment-experienced or treatment-naïve subjects receiving FTC or TDF with other antiretroviral agents in clinical trials included abdominal pain, dyspepsia, vomiting, fever, pain, nasopharyngitis, pneumonia, sinusitis, upper respiratory tract infection, arthralgia, back pain, myalgia, paresthesia, peripheral neuropathy (including peripheral neuritis and neuropathy), anxiety, increased cough, and rhinitis.

Skin discoloration has been reported with higher frequency among FTC-treated subjects; it was manifested by hyperpigmentation on the palms and/or soles and was generally mild and asymptomatic. The mechanism and clinical significance are unknown.

Laboratory Abnormalities in Adult Subjects

The percentage of subjects treated with RPV + FTC/TDF or EFV + FTC/TDF in studies C209 and C215 with selected laboratory abnormalities (Grades 1–4), representing worst-grade toxicity, is presented in Table 2.

Table 2 Selected Laboratory Abnormalities (Grades 1–4) Reported in Adult Subjects Who Received RPV or EFV in Combination with FTC/TDF in Studies C209 and C215 (Week 96 Analysis)
Laboratory Parameter Abnormality | DAIDS Toxicity Range | RPV + FTC/TDF | EFV + FTC/TDF
Laboratory Parameter Abnormality | DAIDS Toxicity Range | N=550 | N=546
BIOCHEMISTRY
Increased Creatinine
Grade 1 | 1.1–1.3 × ULN | 6% | 1%
Grade 2 | >1.3–1.8 × ULN | 1% | 1%
Grade 3 | >1.8–3.4 × ULN | <1% | 0
Grade 4 | >3.4 × ULN | 0 | <1%
Increased AST
Grade 1 | 1.25–2.5 × ULN | 16% | 19%
Grade 2 | >2.5–5.0 × ULN | 4% | 7%
Grade 3 | >5.0–10.0 × ULN | 2% | 3%
Grade 4 | >10.0 × ULN | 1% | 1%
Increased ALT
Grade 1 | 1.25–2.5 × ULN | 19% | 22%
Grade 2 | >2.5–5.0 × ULN | 5% | 7%
Grade 3 | >5.0–10.0 × ULN | 1% | 2%
Grade 4 | >10.0 × ULN | 1% | 1%
Increased Total Bilirubin
Grade 1 | 1.1–1.5 × ULN | 6% | <1%
Grade 2 | >1.5–2.5 × ULN | 3% | 1%
Grade 3 | >2.5–5.0 × ULN | 1% | <1%
Increased Total Cholesterol (fasted)
Grade 1 | 200–239 mg/dL | 14% | 31%
Grade 2 | 240–300 mg/dL | 6% | 18%
Grade 3 | >300 mg/dL | <1% | 2%
Increased LDL Cholesterol (fasted)
Grade 1 | 130–159 mg/dL | 13% | 28%
Grade 2 | 160–190 mg/dL | 5% | 13%
Grade 3 | >190 mg/dL | 1% | 4%
Increased Triglycerides (fasted)
Grade 2 | 500–750 mg/dL | 1% | 2%
Grade 3 | 751–1200 mg/dL | 1% | 2%
Grade 4 | >1200 mg/dL | 0 | 1%
N=number of subjects per treatment group
ULN=Upper limit of normal value.
Note: Percentages were calculated versus the number of subjects in ITT population with FTC + TDF as background regimen.

Emtricitabine or Tenofovir DF: The following Grade 3 or 4 laboratory abnormalities have been previously reported in subjects treated with FTC or TDF with other antiretroviral agents in other clinical trials: increased pancreatic amylase (>2.0 × ULN), increased serum amylase (>175 U/L), increased lipase (>3.0 × ULN), increased alkaline phosphatase (>550 U/L), increased or decreased serum glucose (<40 or >250 mg/dL), increased glycosuria (≥3+), increased creatine kinase (M: >990 U/L; F: >845 U/L), decreased neutrophils (<750/mm^3), and increased hematuria (>75 RBC/HPF).

Adrenal Function: In the pooled Phase 3 trials of C209 and C215, in subjects treated with RPV plus any of the allowed background regimens (N=686), at Week 96 there was an overall mean change from baseline in basal cortisol of –0.69 (−1.12, 0.27) micrograms/dL in the RPV group, and of −0.02 (−0.48, 0.44) micrograms/dL in the EFV group.

In the RPV group, 43/588 (7.3%) of subjects with a normal 250 micrograms ACTH stimulation test at baseline developed an abnormal 250 micrograms ACTH stimulation test (peak cortisol level <18.1 micrograms/dL) during the trial compared to 18/561 (3.2%) in the EFV group. Of the subjects who developed an abnormal 250 micrograms ACTH stimulation test during the trial, 14 subjects in the RPV group and 9 subjects in the EFV group had an abnormal 250 micrograms ACTH stimulation test at Week 96. Overall, there were no serious adverse events, deaths, or treatment discontinuations that could clearly be attributed to adrenal insufficiency. The clinical significance of the higher abnormal rate of 250 micrograms ACTH stimulation tests in the RPV group is not known.

Serum Creatinine: In the pooled Phase 3 trials of C209 and C215 in subjects treated with RPV plus any of the allowed background regimens (N=686), there was a small increase in serum creatinine over 96 weeks of treatment with RPV. Most of this increase occurred within the first 4 weeks of treatment, with a mean change of 0.1 mg/dL (range –0.3 to 0.6 mg/dL) observed through Week 96. In subjects who entered the trial with mild or moderate renal impairment, the serum creatinine increase observed was similar to that seen in subjects with normal renal function. These changes are not considered to be clinically relevant, and no subject discontinued treatment due to increases in serum creatinine. Creatinine increases were comparable by background N(t)RTIs.

Serum Lipids: Changes from baseline in total cholesterol, LDL-cholesterol, and triglycerides are presented in Table 3.

Table 3 Lipid Values Reported in Adult Subjects Receiving RPV or EFV in Combination with FTC/TDF in Studies C209 and C215 [Excludes subjects who received lipid lowering agents during the treatment period.]
 | Pooled Data from the Week 96 Analysis of C209 and C215 Trials
 | RPV + FTC/TDF N=550 |  |  |  | EFV + FTC/TDF N=546
 | N | Baseline | Week 96 |  | N | Baseline | Week 96
Mean |  | Mean (mg/dL) | Mean (mg/dL) | Mean Change [The change from baseline is the mean of within-patient changes from baseline for patients with both baseline and Week 96 values.] (mg/dL) |  | Mean (mg/dL) | Mean (mg/dL) | Mean Change (mg/dL)
Total Cholesterol (fasted) | 430 | 162 | 164 | 2 | 401 | 160 | 186 | 26
HDL-cholesterol (fasted) | 429 | 42 | 45 | 4 | 399 | 40 | 50 | 11
LDL-cholesterol (fasted) | 427 | 97 | 97 | –1 | 397 | 96 | 110 | 14
Triglycerides (fasted) | 430 | 123 | 109 | –14 | 401 | 127 | 133 | 6
N=number of subjects per treatment group

Adult Subjects Coinfected with Hepatitis B and/or Hepatitis C Virus: In adult subjects coinfected with hepatitis B or C virus receiving RPV in studies C209 and C215, the incidence of hepatic enzyme elevation was higher than in subjects receiving RPV who were not coinfected. The same increase was also observed in the EFV arm. The pharmacokinetic exposure of RPV in coinfected subjects was comparable to that in subjects without coinfection.

Adverse Reactions from Clinical Trials Experience in Pediatric Subjects

Emtricitabine: In addition to the adverse reactions reported in adults, anemia and hyperpigmentation were observed in 7% and 32%, respectively, of pediatric subjects (3 months to less than 18 years of age) who received treatment with FTC in the larger of two open-label, uncontrolled pediatric trials (N=116). For additional information, please consult the EMTRIVA® prescribing information.

Rilpivirine: The safety assessment is based on the Week 48 analysis of the single-arm, open-label Phase 2 trial, TMC278-C213, in which 36 antiretroviral treatment-naïve HIV-1-infected subjects 12 to less than 18 years of age and weighing at least 32 kg received RPV (25 mg once daily) in combination with other antiretroviral agents. The median duration of exposure for subjects was 63.5 weeks. No subjects discontinued treatment due to adverse reactions. No new adverse reactions were identified compared to those seen in adults.

Adverse reactions were reported in 19 pediatric subjects (52.8%). Most adverse reactions were Grade 1 or 2. The most common adverse reactions reported in at least 2 subjects (regardless of severity) include headache (19.4%), depression (19.4%), somnolence (13.9%), nausea (11.1%), dizziness (8.3%), abdominal pain (8.3%), vomiting (5.6%), and rash (5.6%).

Observed laboratory abnormalities were comparable to those in adults. For additional information, please consult the Edurant prescribing information.

Adrenal Function

In trial TMC278-C213, at Week 48, the overall mean change from baseline in basal cortisol showed an increase of 1.59 (0.24, 2.93) micrograms/dL.

Six of 30 (20%) subjects with a normal 250 micrograms ACTH stimulation test at baseline developed an abnormal 250 micrograms ACTH stimulation test (peak cortisol level <18.1 micrograms/dL) during the trial. Three of these subjects had an abnormal 250 micrograms ACTH stimulation test at Week 48. Overall, there were no serious adverse events, deaths, or treatment discontinuations that could clearly be attributed to adrenal insufficiency. The clinical significance of the abnormal 250 micrograms ACTH stimulation tests is not known.

Tenofovir DF: In a pediatric clinical trial conducted in subjects 12 to less than 18 years of age, the adverse reactions observed in pediatric subjects who received treatment with TDF were consistent with those observed in clinical trials of TDF in adults [see Warnings and Precautions (5.6)]. For additional information, including information on bone mineral density changes, please consult the VIREAD® prescribing information.

6.2 Postmarketing Experience

The following adverse reactions have been identified during postmarketing experience in patients receiving RPV- or TDF-containing regimens. Because postmarketing reactions are reported voluntarily from a population of uncertain size, it is not always possible to reliably estimate their frequency or establish a causal relationship to drug exposure.

COMPLERA:

Metabolism and Nutrition Disorders
weight increased

Skin and Subcutaneous Tissue Disorders
severe skin and hypersensitivity reactions including DRESS (Drug Reaction with Eosinophilia and Systemic Symptoms)

Rilpivirine:

Renal and Urinary Disorders
nephrotic syndrome

Emtricitabine:

No postmarketing adverse reactions have been identified for inclusion in this section.

Tenofovir DF:

Immune System Disorders
allergic reaction, including angioedema

Metabolism and Nutrition Disorders
lactic acidosis, hypokalemia, hypophosphatemia

Respiratory, Thoracic, and Mediastinal Disorders
dyspnea

Gastrointestinal Disorders
pancreatitis, increased amylase, abdominal pain

Hepatobiliary Disorders
hepatic steatosis, hepatitis, increased liver enzymes (most commonly AST, ALT, gamma GT)

Skin and Subcutaneous Tissue Disorders
rash

Musculoskeletal and Connective Tissue Disorders
rhabdomyolysis, osteomalacia (manifested as bone pain and which may contribute to fractures), muscular weakness, myopathy

Renal and Urinary Disorders
acute renal failure, renal failure, acute tubular necrosis, Fanconi syndrome, proximal renal tubulopathy, interstitial nephritis (including acute cases), nephrogenic diabetes insipidus, renal insufficiency, increased creatinine, proteinuria, polyuria

General Disorders and Administration Site Conditions
asthenia

The following adverse reactions, listed under the body system headings above, may occur as a consequence of proximal renal tubulopathy: rhabdomyolysis, osteomalacia, hypokalemia, muscular weakness, myopathy, hypophosphatemia.

7 DRUG INTERACTIONS

7.1 Not Recommended with Other Antiretroviral Medications

Because COMPLERA is a complete regimen, coadministration with other antiretroviral medications for the treatment of HIV-1 infection is not recommended. Comprehensive information regarding potential drug-drug interactions with other antiretroviral medications is not provided.

This section describes clinically relevant drug interactions with COMPLERA. Drug interaction studies were conducted with the components of COMPLERA (FTC, RPV, and TDF as single agents) or with COMPLERA as a combination product [see Dosage and Administration (2), Contraindications (4), and Clinical Pharmacology (12.3)].

7.2 Drugs Inducing or Inhibiting CYP3A Enzymes

Rilpivirine is primarily metabolized by cytochrome P450 (CYP) 3A, and drugs that induce or inhibit CYP3A may thus affect the clearance of RPV [see Contraindications (4), Warnings and Precautions (5.7), and Clinical Pharmacology (12.3)]. Coadministration of RPV and drugs that induce CYP3A may result in decreased plasma concentrations of RPV and loss of virologic response and possible resistance to RPV or to the class of NNRTIs. Coadministration of RPV and drugs that inhibit CYP3A may result in increased plasma concentrations of RPV.

7.3 Drugs Increasing Gastric pH

Coadministration of RPV with drugs that increase gastric pH may decrease plasma concentrations of RPV and loss of virologic response and possible resistance to RPV or to the class of NNRTIs. Use of RPV with proton pump inhibitors is contraindicated and use of RPV with H2-receptor antagonists requires staggered administration [see Contraindications (4) and Clinical Pharmacology (12.3)].

7.4 Drugs Affecting Renal Function

Because FTC and tenofovir are primarily eliminated by the kidneys through a combination of glomerular filtration and active tubular secretion, coadministration of COMPLERA with drugs that reduce renal function or compete for active tubular secretion may increase serum concentrations of FTC, tenofovir, and/or other renally eliminated drugs. Some examples of drugs that are eliminated by active tubular secretion include, but are not limited to, acyclovir, adefovir dipivoxil, cidofovir, ganciclovir, valacyclovir, valganciclovir, aminoglycosides (e.g., gentamicin), and high-dose or multiple NSAIDs [see Warnings and Precautions (5.5)].

7.5 QT Prolonging Drugs

There is limited information available on the potential for a pharmacodynamic interaction between RPV and drugs that prolong the QTc interval of the electrocardiogram. In a study of healthy subjects, 75 mg once daily and 300 mg once daily doses of RPV (3 times and 12 times the dose in COMPLERA) have been shown to prolong the QTc interval of the electrocardiogram [see Warnings and Precautions (5.7) and Clinical Pharmacology (12.2)]. Consider alternatives to COMPLERA when coadministered with a drug with a known risk of Torsade de Pointes.

7.6 Significant Drug Interactions

Important drug interaction information for COMPLERA is summarized in Table 4. The drug interactions described are based on studies conducted with FTC, RPV, or TDF as individual medications or with COMPLERA as a combination product, or are potential drug interactions [see Clinical Pharmacology (12.3), Tables 9–14]. For list of contraindicated drugs, [see Contraindications (4)].

Table 4 Significant [This table is not all inclusive.] Drug Interactions
Concomitant Drug Class: Drug Name | Effect on Concentration [Increase = ↑; Decrease = ↓; No Effect = ↔] | Clinical Comment
Antacids: antacids (e.g., aluminum, magnesium hydroxide, or calcium carbonate) | ↔ RPV (antacids taken at least 2 hours before or at least 4 hours after RPV) ↓ RPV (concomitant intake) | Administer antacids at least 2 hours before or at least 4 hours after COMPLERA.
Anticonvulsants: carbamazepine oxcarbazepine phenobarbital phenytoin | ↓ RPV | Coadministration is contraindicated due to potential for loss of virologic response and development of resistance.
Antimycobacterials: rifampin rifapentine | ↓ RPV | Coadministration is contraindicated due to potential for loss of virologic response and development of resistance.
rifabutin | ↓ RPV [The interaction was evaluated in a clinical study. All other drug-drug interactions shown are predicted.] | If COMPLERA is coadministered with rifabutin, an additional 25 mg tablet of RPV (Edurant) once per day is recommended to be taken concomitantly with COMPLERA and with a meal for the duration of rifabutin coadministration.
Azole Antifungal Agents: fluconazole itraconazole ketoconazole posaconazole voriconazole | ↑ RPV, [This interaction study has been performed with a dose higher than the recommended dose for RPV assessing the maximal effect on the coadministered drug. The dosing recommendation is applicable to the recommended dose of RPV 25 mg once daily.] ↓ ketoconazole, | No dose adjustment is required when COMPLERA is coadministered with azole antifungal agents. Clinically monitor for breakthrough fungal infections when azole antifungals are coadministered with COMPLERA.
Glucocorticoid (systemic): dexamethasone (more than a single-dose treatment) | ↓ RPV | Coadministration is contraindicated due to potential for loss of virologic response and development of resistance.
Hepatitis C Antiviral Agents: ledipasvir/sofosbuvir sofosbuvir/velpatasvir sofosbuvir/velpatasvir/voxilaprevir | ↑ tenofovir | Patients receiving COMPLERA concomitantly with HARVONI® (ledipasvir/sofosbuvir), EPCLUSA® (sofosbuvir/velpatasvir), or VOSEVI® (sofosbuvir/velpatasvir/voxilaprevir) should be monitored for adverse reactions associated with TDF.
H2-Receptor Antagonists: cimetidine famotidine nizatidine ranitidine | ↔ RPV, (famotidine taken 12 hours before RPV or 4 hours after RPV) ↓ RPV, (famotidine taken 2 hours before RPV) | Administer H2-receptor antagonists at least 12 hours before or at least 4 hours after COMPLERA.
Herbal Products: St John's wort (Hypericum perforatum) | ↓ RPV | Coadministration is contraindicated due to potential for loss of virologic response and development of resistance.
Macrolide or Ketolide Antibiotics: clarithromycin erythromycin telithromycin | ↑ RPV ↔ clarithromycin ↔ erythromycin ↔ telithromycin | Where possible, alternatives such as azithromycin should be considered.
Narcotic Analgesics: methadone | ↓ R(–) methadone ↓ S(+) methadone ↔ RPV ↔ methadone (when used with tenofovir) | No dose adjustments are required when initiating coadministration of methadone with COMPLERA. However, clinical monitoring is recommended as methadone maintenance therapy may need to be adjusted in some patients.
Proton Pump Inhibitors: e.g., dexlansoprazole esomeprazole lansoprazole omeprazole pantoprazole rabeprazole | ↓ RPV | Coadministration is contraindicated due to potential for loss of virologic response and development of resistance.

7.7 Drugs with No Observed Interactions with COMPLERA

No clinically significant drug interactions have been observed between FTC and the following medications: famciclovir, ledipasvir/sofosbuvir, sofosbuvir/velpatasvir, sofosbuvir/velpatasvir/voxilaprevir, or TDF.

No clinically significant drug interactions have been observed between TDF and the following medications: entecavir, methadone, oral contraceptives, ribavirin, sofosbuvir, or tacrolimus in studies conducted in healthy subjects.

No clinically significant drug interactions have been observed between RPV and the following medications: acetaminophen, atorvastatin, chlorzoxazone, ethinyl estradiol, ledipasvir/sofosbuvir, norethindrone, sildenafil, simeprevir, sofosbuvir, sofosbuvir/velpatasvir, sofosbuvir/velpatasvir/voxilaprevir, or TDF. RPV did not have a clinically significant effect on the pharmacokinetics of digoxin or metformin.

8 USE IN SPECIFIC POPULATIONS

8.1 Pregnancy

Pregnancy Exposure Registry

There is a pregnancy exposure registry that monitors pregnancy outcomes in individuals exposed to COMPLERA during pregnancy. Healthcare providers are encouraged to register patients by calling the Antiretroviral Pregnancy Registry (APR) at 1-800-258-4263.

Risk Summary

Available data from the APR show no increase in the overall risk of major birth defects with first trimester exposure for emtricitabine (FTC), rilpivirine (RPV), or tenofovir (TDF) compared with the background rate for major birth defects of 2.7% in a U.S. reference population of the Metropolitan Atlanta Congenital Defects Program (MACDP) (see Data). In a clinical trial, total rilpivirine exposures were generally lower during pregnancy compared to the postpartum period [see Clinical Pharmacology (12.3)]. The rate of miscarriage for individual drugs is not reported in the APR. The estimated background rate of miscarriage in clinically recognized pregnancies in the U.S. general population is 15–20%.

Based on the experience of HIV-1-infected pregnant individuals who completed a clinical trial through the postpartum period with an RPV-based regimen, no dose adjustments are required for pregnant patients who are already on a stable RPV-containing regimen prior to pregnancy and who are virologically suppressed (HIV-1 RNA less than 50 copies per mL). Lower exposures of RPV were observed during pregnancy, therefore viral load should be monitored closely [see Data and Clinical Pharmacology (12.3)].

In animal studies, no adverse developmental effects were observed when the components of COMPLERA were administered separately during the period of organogenesis at exposures up to 60 and 120 times (mice and rabbits, respectively, FTC) and 15 and 70 times (rats and rabbits, respectively; RPV) the exposure of these components in COMPLERA and at 14 and 19 times (rats and rabbits, respectively) the human dose of TDF based on body surface area comparisons (see Data). Likewise, no adverse developmental effects were seen when FTC was administered to mice and RPV was administered to rats through lactation at exposures up to approximately 60 and 63 times, respectively, the exposure at the recommended daily dose of these components in COMPLERA. No adverse effects were observed in the offspring of rats when TDF was administered through lactation at tenofovir exposures of approximately 14 times the exposure at the recommended daily dosage of COMPLERA.

Data

Human Data

Prospective reports from the APR of overall major birth defects in pregnancies exposed to drug components of COMPLERA are compared with a U.S. background major birth defect rate. Methodological limitations of the APR include the use of MACDP as the external comparator group. Limitations of using an external comparator include differences in methodology and populations, as well as confounding due to the underlying disease.

Emtricitabine: Based on prospective reports to the APR of exposures to FTC-containing regimens during pregnancy resulting in live births (including over 2,750 exposed in the first trimester and over 1,200 exposed in the second/third trimester), there was no increase in overall major birth defects with FTC compared with the background birth defect rate of 2.7% in the U.S. reference population of the MACDP. The prevalence of major birth defects in live births was 2.4% (95% CI: 1.9% to 3.1%) with first trimester exposure to FTC-containing regimens and 2.3% (95% CI: 1.5% to 3.3%) with the second/third trimester exposure to FTC-containing regimens.

Rilpivirine: RPV in combination with a background regimen was evaluated in a clinical trial of 19 HIV-1 infected pregnant subjects on an RPV-based regimen during the second and third trimesters and postpartum. Each of the subjects were on an RPV-based regimen at the time of enrollment. Twelve subjects completed the trial through the postpartum period (6–12 weeks after delivery) and pregnancy outcomes are missing for six subjects. The exposure (C0h and AUC) of total RPV was approximately 30 to 40% lower during pregnancy compared with postpartum (6 to 12 weeks). The protein binding of RPV was similar (>99%) during second trimester, third trimester, and postpartum period [see Clinical Pharmacology (12.3)]. One subject discontinued the trial following fetal death at 25 weeks gestation due to suspected premature rupture of membranes. Among the 12 subjects who were virologically suppressed at baseline (less than 50 copies/mL), virologic response was preserved in 10 subjects (83.3%) through the third trimester visit and in 9 subjects (75%) through the 6–12 week postpartum visit. Virologic outcomes during the third trimester visit were missing for two subjects who were withdrawn (one subject was nonadherent to the study drug and one subject withdrew consent). Among the 10 infants with available HIV test results, all were negative for HIV-1 at the time of delivery and up to 16 weeks postpartum (all 10 infants received prophylactic treatment with zidovudine). RPV was well tolerated during pregnancy and postpartum. There were no new safety findings compared with the known safety profile of RPV in HIV–1-infected adults.

Based on prospective reports to the APR of exposures to RPV-containing regimens during pregnancy (including over 290 exposed during first trimester and over 160 exposed in the second/third trimester), there was no significant increase in overall risk of major birth defects with RPV compared to the background birth defect rate of 2.7% in the U.S. reference population of the MACDP. The prevalence of major birth defects in live births was 1.0% (95% CI: 0.2% to 2.9%) and 1.2% (95% CI: 0.2% to 4.4%) following first and second/third trimester exposure, respectively, to RPV-containing regimens.

Tenofovir DF: Based on prospective reports to the APR of exposures to TDF-containing regimens during pregnancy resulting in live births (including over 3,500 exposed in the first trimester and over 1,500 exposed in the second/third trimester), there was no increase in overall risk of major birth defects compared with the background birth defect rate of 2.7% in the U.S. reference population of the MACDP. The prevalence of major birth defects in live births was 2.3% (95% CI: 1.8% to 2.9%) with first trimester exposure to TDF-containing regimens, and 2.2% (95% CI: 1.6% to 3.1%) with the second/third trimester exposure to TDF-containing regimens.

Animal Data

Emtricitabine: FTC was administered orally to pregnant mice (at 0, 250, 500, or 1,000 mg/kg/day), and rabbits (at 0, 100, 300, or 1,000 mg/kg/day) through organogenesis (on gestation days 6 through 15, and 7 through 19, respectively). No significant toxicological effects were observed in embryo-fetal toxicity studies performed with FTC in mice at exposures (AUC) approximately 60 times higher and in rabbits at approximately 120 times higher than human exposures at the recommended daily dose. In a pre/postnatal development study in mice, FTC was administered orally at doses up to 1,000 mg/kg/day; no significant adverse effects directly related to drug were observed in the offspring exposed daily from before birth (in utero) through sexual maturity at daily exposures (AUC) of approximately 60 times higher than human exposures at the recommended daily dose.

Rilpivirine: RPV was administered orally to pregnant rats (40, 120, or 400 mg/kg/day) and rabbits (5, 10, or 20 mg/kg/day) through organogenesis (on gestation days 6 through 17, and 6 through 19, respectively). No significant toxicological effects were observed in embryo-fetal toxicity studies performed with RPV in rats and rabbits at exposures 15 (rats) and 70 (rabbits) times higher than the exposure in humans at the recommended dose of 25 mg once daily. In a pre/postnatal development study with RPV, where rats were administered up to 400 mg/kg/day through lactation, no significant adverse effects directly related to drug were noted in the offspring.

Tenofovir DF: TDF was administered orally to pregnant rats (at 0, 50, 150, or 450 mg/kg/day) and rabbits (at 0, 30, 100, or 300 mg/kg/day) through organogenesis (on gestation days 7 through 17, and 6 through 18, respectively). No significant toxicological effects were observed in embryo-fetal toxicity studies performed with TDF in rats at doses up to 14 times the human dose based on body surface area comparisons and in rabbits at doses up to 19 times the human dose based on body surface area comparisons. In a pre/postnatal development study in rats, TDF was administered orally through lactation at doses up to 600 mg/kg/day; no adverse effects were observed in the offspring at tenofovir exposures of approximately 2.7 times higher than human exposures at the recommended daily dose of COMPLERA.

8.2 Lactation

Risk Summary

The Centers for Disease Control and Prevention recommend that HIV infected mothers not breastfeed their infants to avoid risking postnatal transmission of HIV.

Based on published data, FTC and tenofovir have been shown to be present in human milk. There are no data on the presence of RPV in human milk. RPV has been shown to be present in rat milk (see Data).

It is not known if the components of COMPLERA affect milk production or have effects on the breastfed child. Because of the potential for: (1) HIV transmission (in HIV-negative infants); (2) developing viral resistance (in HIV-positive infants); and (3) adverse reactions in a breastfed infant similar to those seen in adults, instruct mothers not to breastfeed if they are receiving COMPLERA.

Data

Rilpivirine: In animals, no studies have been conducted to assess the excretion of RPV directly; however RPV was measured in rat pups which were exposed through the milk of treated dams (dosed up to 400 mg/kg/day).

8.4 Pediatric Use

The safety and effectiveness of COMPLERA as a complete regimen for the treatment of HIV-1 infection was established in pediatric subjects 12 years of age and older with body weight greater than or equal to 35 kg [see Dosage and Administration (2.2)]. Use of COMPLERA in this age group weighing at least 35 kg is supported by adequate and well-controlled studies of RPV+FTC+TDF in adults with HIV-1 infection as well as data from pediatric studies of the individual components of COMPLERA (RPV, FTC, and TDF) [see Clinical Pharmacology (12.3), and Clinical Studies (14.2)].

COMPLERA should only be administered to pediatric patients with a body weight greater than or equal to 35 kg. Because COMPLERA is a fixed-dose combination tablet, the dose of COMPLERA cannot be adjusted for patients of lower weight. Safety and effectiveness for COMPLERA have not been established in pediatric patients weighing less than 35 kg [see Adverse Reactions (6.1) and Clinical Pharmacology (12.3)].

8.5 Geriatric Use

Clinical studies of FTC, RPV, or TDF did not include sufficient numbers of subjects aged 65 and over to determine whether they respond differently from younger subjects. In general, dose selection for elderly patients should be cautious, keeping in mind the greater frequency of decreased hepatic, renal, or cardiac function, and of concomitant disease or other drug therapy [see Clinical Pharmacology (12.3)].

8.6 Renal Impairment

Because COMPLERA is a fixed-dose combination, and cannot be dose adjusted, it is not recommended in patients with moderate, severe, or end-stage renal impairment (estimated creatinine clearance below 50 mL per minute) or that require dialysis [see Warnings and Precautions (5.5) and Clinical Pharmacology (12.3)].

8.7 Hepatic Impairment

No dose adjustment of COMPLERA is required in patients with mild (Child-Pugh Class A) or moderate (Child-Pugh Class B) hepatic impairment. COMPLERA has not been studied in patients with severe hepatic impairment (Child-Pugh Class C) [see Clinical Pharmacology (12.3)].

10 OVERDOSAGE

If overdose occurs the patient must be monitored for evidence of toxicity. Treatment of overdose with COMPLERA consists of general supportive measures, including monitoring of vital signs and ECG (QT interval) as well as observation of the clinical status of the patient.

Emtricitabine: Hemodialysis treatment removes approximately 30% of the FTC dose over a 3-hour dialysis period starting within 1.5 hours of FTC dosing (blood flow rate of 400 mL per minute and a dialysate flow rate of 600 mL per minute). It is not known whether FTC can be removed by peritoneal dialysis.

Rilpivirine: There is no specific antidote for overdose with RPV. Human experience of overdose with RPV is limited. Since RPV is highly bound to plasma protein, dialysis is unlikely to result in significant removal of RPV.

Tenofovir DF: Tenofovir is efficiently removed by hemodialysis with an extraction coefficient of approximately 54%. Following a single 300 mg dose of TDF, a 4-hour hemodialysis session removed approximately 10% of the administered tenofovir dose.

11 DESCRIPTION

COMPLERA is a fixed-dose combination tablet containing FTC, rilpivirine hydrochloride, and TDF. Emtricitabine (FTC) is a synthetic nucleoside analog of cytidine. Rilpivirine (RPV) is a non-nucleoside reverse transcriptase inhibitor. Tenofovir disoproxil fumarate (TDF) is converted in vivo to tenofovir, an acyclic nucleoside phosphonate (nucleotide) analog of adenosine 5′-monophosphate.

COMPLERA tablets are for oral administration. Each tablet contains 200 mg of FTC, 27.5 mg of rilpivirine hydrochloride (equivalent to 25 mg of RPV), and 300 mg of TDF (equivalent to 245 mg of tenofovir disoproxil) as active ingredients. The tablets include the following inactive ingredients: croscarmellose sodium, lactose monohydrate, magnesium stearate, microcrystalline cellulose, polysorbate 20, povidone, pregelatinized starch. The tablets are film coated with a coating material containing FD&C Blue #2 aluminum lake, FD&C Yellow #6 aluminum lake, hypromellose, iron oxide red, lactose monohydrate, polyethylene glycol, titanium dioxide, triacetin.

Emtricitabine: The chemical name of FTC is 5-fluoro-1-[(2R,5S)-2-(hydroxymethyl)-1,3-oxathiolan-5-yl]cytosine. Emtricitabine is the (-) enantiomer of a thio analog of cytidine, which differs from other cytidine analogs in that it has a fluorine in the 5-position.

It has a molecular formula of C8H10FN3O3S and a molecular weight of 247.24. It has the following structural formula:

FTC is a white to off-white crystalline powder with a solubility of approximately 112 mg per mL in water at 25 °C.

Rilpivirine: RPV is available as the hydrochloride salt. The chemical name for rilpivirine hydrochloride is 4-[[4-[[4-[(E)-2-cyanoethenyl]-2,6-dimethylphenyl]amino]-2-pyrimidinyl]amino]benzonitrile monohydrochloride. Its molecular formula is C22H18N6 ∙ HCl and its molecular weight is 402.88. Rilpivirine hydrochloride has the following structural formula:

Rilpivirine hydrochloride is a white to almost white powder. Rilpivirine hydrochloride is practically insoluble in water over a wide pH range.

Tenofovir DF: TDF is a fumaric acid salt of the bis-isopropoxycarbonyloxymethyl ester derivative of tenofovir. The chemical name of TDF is 9-[(R)-2 [[bis[[(isopropoxycarbonyl)oxy]- methoxy]phosphinyl]methoxy]propyl]adenine fumarate (1:1). It has a molecular formula of C19H30N5O10P ∙ C4H4O4 and a molecular weight of 635.52. It has the following structural formula:

TDF is a white to off-white crystalline powder with a solubility of 13.4 mg per mL in water at 25 °C. All dosages are expressed in terms of TDF except where otherwise noted.

12 CLINICAL PHARMACOLOGY

12.1 Mechanism of Action

COMPLERA is a fixed-dose combination of the antiretroviral drugs FTC, RPV, and TDF [see Microbiology (12.4)].

12.2 Pharmacodynamics

Effects on Electrocardiogram

The effect of RPV at the recommended dose of 25 mg once daily on the QTcF interval was evaluated in a randomized, placebo-, and active- (moxifloxacin 400 mg once daily) controlled crossover study in 60 healthy adults, with 13 measurements over 24 hours at steady state. The maximum mean time-matched (95% upper confidence bound) differences in QTcF interval from placebo after baseline correction was 2.0 (5.0) milliseconds (i.e., below the threshold of clinical concern).

When doses of 75 mg once daily and 300 mg once daily of RPV (3 times and 12 times the dose in COMPLERA) were studied in healthy adults, the maximum mean time-matched (95% upper confidence bound) differences in QTcF interval from placebo after baseline correction were 10.7 (15.3) and 23.3 (28.4) milliseconds, respectively. Steady-state administration of RPV 75 mg once daily and 300 mg once daily resulted in a mean steady-state Cmax approximately 2.6-fold and 6.7-fold, respectively, higher than the mean Cmax observed with the recommended 25 mg once daily dose of RPV [see Warnings and Precautions (5.7)].

12.3 Pharmacokinetics

COMPLERA: Under fed conditions (total calorie content of the meal was approximately 400 kcal with approximately 13 grams of fat), RPV, FTC, and tenofovir exposures were similar when comparing COMPLERA to EMTRIVA capsules (200 mg) plus Edurant tablets (25 mg) plus VIREAD tablets (300 mg) following single-dose administration to healthy subjects (N=34).

Single-dose administration of COMPLERA tablets to healthy subjects under fasted conditions provided approximately 25% higher exposure of RPV compared to administration of EMTRIVA capsules (200 mg) plus Edurant tablets (25 mg) plus VIREAD tablets (300 mg), while exposures of FTC and tenofovir were comparable (N=15).

Absorption, Distribution, Metabolism, and Excretion

The pharmacokinetic properties of the components of COMPLERA are provided in Table 5. The PK parameters of RPV, FTC, and tenofovir are provided in Table 6.

Table 5 Pharmacokinetic Properties of the Components of COMPLERA
 | RPV | FTC | Tenofovir
Absorption
Tmax (h) | 4–5 | 1–2 | 1
% Fasted oral bioavailability [Median] | NC | 93 | 25 [Oral bioavailability of tenofovir from VIREAD.]
Effect of a light meal (relative to fasting) [Values refer to % change based on calculated geometric mean ratio [fed/fasted] in AUC. COMPLERA light meal = 390 kcal, 12 g fat; COMPLERA standard meal = 540 kcal, 21 g fat. High fat meal not evaluated. Increase = ↑; Decrease = ↓; No Effect= ↔] | ↑9% | ↔ | ↑28%
Effect of a standard meal (relative to fasting) | ↑16% | ↔ | ↑38%
Distribution
% Bound to human plasma proteins | ~99 | <4 | <0.7
Source of protein binding data | In vitro | In vitro | In vitro
Metabolism
Metabolism | CYP3A | Not significantly metabolized
Elimination
Major route of elimination | Metabolism | Glomerular filtration and active tubular secretion
CLrenal [Mean ± SD] (mL/min) | NC | 213±89 | 243±33
t1/2 (h) [t1/2 values refer to median terminal plasma half-life.] | 50 | 10 | 17
% Of dose excreted in urine [Dosing in mass balance studies: FTC (single dose administration of [^14C] FTC after multiple dosing of FTC for 10 days); RPV (single dose administration of [^14C] RPV); mass balance study not conducted for tenofovir.] | 6 | 86 | 70−80
% Of dose excreted in feces | 85 | ~14 | NC
NC=Not Calculated

Table 6 Pharmacokinetic Parameters for RPV, FTC, and Tenofovir in HIV-Infected Adults
Parameter Mean ± SD | RPV [Population PK estimates of RPV 25 mg once daily in antiretroviral treatment-naïve HIV-1-infected adult subjects (pooled data from Phase 3 trials through Week 96; n=679)] | FTC [Multiple-dose oral administration of FTC 200 mg to HIV-1-infected subjects (n=20)] | Tenofovir [Single 300 mg dose of TDF to HIV-1-infected subjects in the fasted state]
Cmax (μg/mL) | NA | 1.80±0.72 [Data presented as steady state values] | 0.30±0.09
AUCtau (μg∙hr/mL) | 2.24±0.85 | 10.0±3.12 | 2.29±0.69 [AUC0–24h]
C0h (μg/mL) | 0.08±0.04 | 0.09±0.07 | NA
NA=Not Applicable; SD=Standard Deviation

Specific Populations

Geriatric Patients

The pharmacokinetics of FTC, RPV, and tenofovir have not been fully evaluated in the elderly (65 years of age and older) [see Use in Specific Populations (8.5)].

Pediatric Patients

Pediatric trials have not been conducted using COMPLERA tablets. Pediatric information is based on trials conducted with the individual components of COMPLERA [see Use in Specific Populations (8.4)].

Emtricitabine: The pharmacokinetics of FTC at steady state were determined in 27 HIV-1-infected pediatric subjects 13 to 17 years of age receiving a daily dose of 6 mg/kg up to a maximum dose of 240 mg oral solution or a 200 mg capsule; 26 of 27 subjects in this age group received the 200 mg FTC capsule. Mean (± SD) Cmax and AUC were 2.7 ± 0.9 μg/mL and 12.6 ± 5.4 μg∙hr/mL, respectively. Exposures achieved in pediatric subjects 12 to less than 18 years of age were similar to those achieved in adults receiving a once daily dose of 200 mg.

Rilpivirine: The pharmacokinetics of RPV in antiretroviral treatment-naïve HIV-1- infected pediatric subjects 12 to less than 18 years of age receiving RPV 25 mg once daily were comparable to those in treatment-naïve HIV-1-infected adults receiving RPV 25 mg once daily (See Table 7). There was no clinically significant impact of body weight on RPV pharmacokinetics in pediatric subjects in trial C213 (33 to 93 kg).

Table 7 Population Pharmacokinetic Estimates of RPV 25 mg once daily in Antiretroviral Treatment-Naïve HIV-1-Infected Pediatric Subjects aged 12 to less than 18 years (Data from Phase 2 Trial through Week 48)
Parameter | RPV 25 mg once daily N=34
AUC24h (ng∙h/mL)
Mean ± Standard Deviation | 2424 ± 1024
Median (Range) | 2269 (417−5166)
C0h (ng/mL)
Mean ± Standard Deviation | 85 ± 40
Median (Range) | 79 (7−202)

Tenofovir DF: Steady-state pharmacokinetics of tenofovir were evaluated in 8 HIV-1-infected pediatric subjects (12 to less than 18 years). Mean (± SD) Cmax and AUCtau are 0.38 ± 0.13 μg/mL and 3.39 ± 1.22 μg∙hr/mL, respectively. Tenofovir exposure achieved in these pediatric subjects receiving oral daily doses of TDF 300 mg was similar to exposures achieved in adults receiving once-daily doses of TDF 300 mg.

Gender

No clinically relevant pharmacokinetic differences have been observed based on gender for FTC, RPV, and TDF.

Race

Emtricitabine: No pharmacokinetic differences due to race have been identified following the administration of FTC.

Rilpivirine: Population pharmacokinetic analysis of RPV in HIV-1-infected subjects indicated that race had no clinically relevant effect on the exposure to RPV.

Tenofovir DF: There were insufficient numbers from racial and ethnic groups other than Caucasian to adequately determine potential pharmacokinetic differences among these populations following the administration of TDF.

Patients with Renal Impairment

Emtricitabine and Tenofovir DF: The pharmacokinetics of FTC and TDF are altered in subjects with renal impairment. In subjects with creatinine clearance below 50 mL per minute or with end stage renal disease requiring dialysis, Cmax and AUC of FTC and tenofovir were increased [see Warnings and Precautions (5.5) and Use in Specific Populations (8.6)].

Rilpivirine: Population pharmacokinetic analysis indicated that RPV exposure was similar in HIV-1-infected subjects with mild renal impairment relative to HIV-1-infected subjects with normal renal function. There is limited or no information regarding the pharmacokinetics of RPV in patients with moderate or severe renal impairment or in patients with end-stage renal disease, and RPV concentrations may be increased due to alteration of drug absorption, distribution, and metabolism secondary to renal dysfunction [see Use in Specific Populations (8.6)].

Patients with Hepatic Impairment

Emtricitabine: The pharmacokinetics of FTC have not been studied in subjects with hepatic impairment; however, FTC is not significantly metabolized by liver enzymes, so the impact of liver impairment should be limited.

Rilpivirine: RPV is primarily metabolized and eliminated by the liver. In a study comparing 8 subjects with mild hepatic impairment (Child-Pugh score A) to 8 matched controls, and 8 subjects with moderate hepatic impairment (Child-Pugh score B) to 8 matched controls, the multiple dose exposure of RPV was 47% higher in subjects with mild hepatic impairment and 5% higher in subjects with moderate hepatic impairment. RPV has not been studied in subjects with severe hepatic impairment (Child-Pugh score C) [see Use in Specific Populations (8.7)].

Tenofovir DF: The pharmacokinetics of tenofovir following a 300 mg dose of TDF have been studied in non-HIV-infected subjects with moderate to severe hepatic impairment. There were no substantial alterations in tenofovir pharmacokinetics in subjects with hepatic impairment compared with unimpaired subjects.

Hepatitis B and/or Hepatitis C Virus Coinfection

The pharmacokinetics of FTC and TDF have not been fully evaluated in hepatitis B and/or C virus-coinfected patients. Population pharmacokinetic analysis indicated that hepatitis B and/or C virus coinfection had no clinically relevant effect on the exposure to RPV.

Pregnancy and Postpartum

The exposure (C0h and AUC24h) to total RPV after intake of RPV 25 mg once daily as part of an antiretroviral regimen was 30 to 40% lower during pregnancy (similar for the second and third trimester), compared with postpartum (see Table 8). However, the exposure during pregnancy was not significantly different from exposures obtained in Phase 3 trials of RPV-containing regimens. Based on the exposure-response relationship for RPV, this decrease is not considered clinically relevant in patients who are virologically suppressed. The protein binding of RPV was similar (>99%) during the second trimester, third trimester, and postpartum.

Table 8: Pharmacokinetic Results of Total RPV After Administration of RPV 25 mg Once Daily as Part of an Antiretroviral Regimen, During the 2nd Trimester of Pregnancy, the 3rd Trimester of Pregnancy and Postpartum
Pharmacokinetics of total RPV (mean ±SD, tmax: median [range]) | Postpartum (6–12 Weeks) (n=11) | 2nd Trimester of pregnancy (n=15) | 3rd Trimester of pregnancy (n=13)
C0h, ng/mL | 111 ± 69.2 | 65.0 ± 23.9 | 63.5 ± 26.2
Cmin, ng/mL | 84.0 ± 58.8 | 54.3 ± 25.8 | 52.9 ± 24.4
Cmax, ng/mL | 167 ± 101 | 121 ± 45.9 | 123 ± 47.5
tmax, h | 4.00 (2.03−25.08) | 4.00 (1.00−9.00) | 4.00 (2.00−24.93)
AUC24h, ng∙h/mL | 2,714 ± 1,535 | 1,792 ± 711 | 1,762 ± 662

Drug Interaction Studies

Rilpivirine: RPV is primarily metabolized by cytochrome CYP3A, and drugs that induce or inhibit CYP3A may thus affect the clearance of RPV. Coadministration of COMPLERA and drugs that induce CYP3A may result in decreased plasma concentrations of RPV and loss of virologic response and possible resistance. Coadministration of COMPLERA and drugs that inhibit CYP3A may result in increased plasma concentrations of RPV. Coadministration of COMPLERA with drugs that increase gastric pH may result in decreased plasma concentrations of RPV and loss of virologic response and possible resistance to RPV and to the class of NNRTIs.

RPV at a dose of 25 mg once daily is not likely to have a clinically relevant effect on the exposure of medicinal products metabolized by CYP enzymes.

Emtricitabine and Tenofovir DF: In vitro and clinical pharmacokinetic drug-drug interaction studies have shown that the potential for CYP-mediated interactions involving FTC and tenofovir with other medicinal products is low.

FTC and tenofovir are primarily excreted by the kidneys by a combination of glomerular filtration and active tubular secretion. No drug-drug interactions due to competition for renal excretion have been observed; however, coadministration of FTC and TDF with drugs that are eliminated by active tubular secretion may increase concentrations of FTC, tenofovir, and/or the coadministered drug [see Drug Interactions (7.4, 7.6)].

Drugs that decrease renal function may increase concentrations of FTC and/or tenofovir.

The drug interaction studies described in Tables 9–14 were conducted with COMPLERA (RPV/FTC/TDF) or the components of COMPLERA (RPV, FTC, or TDF) administered individually.

The effects of coadministration of other drugs on the AUC, Cmax, and Cmin values of RPV, FTC, and TDF are summarized in Tables 9, 10, and 11, respectively. The effect of coadministration of RPV, FTC, and TDF on the AUC, Cmax, and Cmin values of other drugs are summarized in Tables 12, 13, and 14, respectively. For information regarding clinical recommendations, see Drug Interactions (7).

Table 9 Drug Interactions: Changes in Pharmacokinetic Parameters for RPV in the Presence of the Coadministered Drugs
Coadministered Drug | Dose of Coadministered Drug (mg) | RPV Dose (mg) | N [N=maximum number of subjects for Cmax, AUC, or Cmin] | Mean % Change of RPV Pharmacokinetic Parameters [Increase = ↑; Decrease = ↓; No Effect = ↔] (90% CI)
Coadministered Drug | Dose of Coadministered Drug (mg) | RPV Dose (mg) | N [N=maximum number of subjects for Cmax, AUC, or Cmin] | Cmax | AUC | Cmin
Acetaminophen | 500 single dose | 150 once daily [The interaction study has been performed with a dose higher than the recommended dose for RPV (25 mg once daily) assessing the maximal effect on the coadministered drug.] | 16 | ↑9 (↑1 to ↑18) | ↑16 (↑10 to ↑22) | ↑26 (↑16 to ↑38)
Atorvastatin | 40 once daily | 150 once daily | 16 | ↓9 (↓21 to ↑6) | ↓10 (↓19 to ↓1) | ↓10 (↓16 to ↓4)
Chlorzoxazone | 500 single dose taken 2 hours after RPV | 150 once daily | 16 | ↑17 (↑8 to ↑27) | ↑25 (↑16 to ↑35) | ↑18 (↑9 to ↑28)
Ethinyl Estradiol/ Norethindrone | 0.035 once daily/1 once daily | 25 once daily | 16 | ↔ [Study conducted with COMPLERA (RPV/FTC/TDF) coadministered with HARVONI (ledipasvir/sofosbuvir).] | ↔ | ↔
Famotidine | 40 single dose taken 12 hours before RPV | 150 single dose | 24 | ↓1 (↓16 to ↑16) | ↓9 (↓22 to ↑7) | NA
Famotidine | 40 single dose taken 2 hours before RPV | 150 single dose | 23 | ↓85 (↓88 to ↓81) | ↓76 (↓80 to ↓72) | NA
Famotidine | 40 single dose taken 4 hours after RPV | 150 single dose | 24 | ↑21 (↑6 to ↑39) | ↑13 (↑1 to ↑27) | NA
Ketoconazole | 400 once daily | 150 once daily | 15 | ↑30 (↑13 to ↑48) | ↑49 (↑31 to ↑70) | ↑76 (↑57 to ↑97)
Ledipasvir/ Sofosbuvir | 90/400 once daily | 25 once daily | 14 | ↓3 (↓12 to ↑7) | ↑2 (↓6 to ↑11) | ↑12 (↑3 to ↑21)
Methadone | 60–100 once daily individualized dose | 25 once daily | 12 | ↔ [Comparison based on historic controls.] | ↔ | ↔
Omeprazole | 20 once daily | 150 once daily | 16 | ↓40 (↓52 to ↓27) | ↓40 (↓49 to ↓29) | ↓33 (↓42 to ↓22)
Rifabutin | 300 once daily | 25 once daily | 18 | ↓31 (↓38 to ↓24) | ↓42 (↓48 to ↓35) | ↓48 (↓54 to ↓41)
Rifabutin | 300 once daily | 50 once daily | 18 | ↑43 (↑30 to ↑56) [Reference arm for comparison was 25 mg q.d. RPV administered alone.] | ↑16 (↑6 to ↑26) | ↓7 (↓15 to↑1)
Rifampin | 600 once daily | 150 once daily | 16 | ↓69 (↓73 to ↓64) | ↓80 (↓82 to ↓77) | ↓89 (↓90 to ↓87)
Simeprevir | 25 once daily | 150 once daily | 23 | ↑ 4 (↓ 5 to ↑ 13) | ↑ 12 (↑ 5 to ↑ 19) | ↑ 25 (↑ 16 to ↑ 35)
Sildenafil | 50 single dose | 75 once daily | 16 | ↓8 (↓15 to ↓1) | ↓2 (↓8 to ↑5) | ↑4 (↓2 to ↑9)
Sofosbuvir/ Velpatasvir | 400/100 once daily | 25 once daily [Study conducted with COMPLERA coadministered with EPCLUSA (sofosbuvir/velpatasvir).] | 24 | ↓7 (↓12 to ↓2) | ↓5 (↓10 to 0) | ↓4 (↓10 to ↑3)
Sofosbuvir/ Velpatasvir/ Voxilaprevir [Study conducted with ODEFSEY® (FTC/RPV/tenofovir alafenamide).] | 400/100/100 + 100 voxilaprevir [Study conducted with additional voxilaprevir 100 mg to achieve voxilaprevir exposures expected in HCV-infected patients.] once daily | 25 once daily | 30 | ↓21 (↓26 to ↓16) | ↓20 (↓24 to ↓15) | ↓18 (↓23 to ↓13)
TDF | 300 once daily | 150 once daily | 16 | ↓4 (↓19 to ↑13) | ↑1 (↓13 to ↑18) | ↓1 (↓17 to ↑16)
NA=not available

Table 10 Drug Interactions: Changes in Pharmacokinetic Parameters for FTC in the Presence of the Coadministered Drugs
Coadministered Drug | Dose of Coadministered Drug (mg) | FTC Dose (mg) | N [N=maximum number of subjects for Cmax, AUC, or Cmin] | Mean % Change of FTC Pharmacokinetic Parameters [Increase = ↑; Decrease = ↓; No Effect = ↔] (90% CI)
Coadministered Drug | Dose of Coadministered Drug (mg) | FTC Dose (mg) | N [N=maximum number of subjects for Cmax, AUC, or Cmin] | Cmax | AUC | Cmin
Famciclovir | 500 × 1 | 200 × 1 | 12 | ↔ | ↔ | NA
Ledipasvir/ Sofosbuvir | 90/400 once daily | 200 once daily [Study conducted with COMPLERA coadministered with HARVONI.] | 15 | ↑2 (↓2 to ↑6) | ↑5 (↑2 to ↑8) | ↑6 (↓3 to ↑15)
Sofosbuvir/ Velpatasvir | 400/100 once daily | 200 once daily [Study conducted with COMPLERA coadministered with EPCLUSA.] | 24 | ↓5 (↓10 to 0) | ↓1 (↓3 to ↑2) | ↑5 (↓1 to ↑11)
Sofosbuvir/ Velpatasvir/ Voxilaprevir | 400/100/100 + Voxilaprevir [Study conducted with additional voxilaprevir 100 mg to achieve voxilaprevir exposures expected in HCV-infected patients.] 100 once daily | 200 once daily [Study conducted with ODEFSEY (FTC/RPV/tenofovir alafenamide).] | 30 | ↓12 (↓17 to ↓7) | ↓7 (↓10 to ↓4) | ↑7 (↑1 to ↑14)
TDF | 300 once daily × 7 days | 200 once daily × 7 days | 17 | ↔ | ↔ | ↑ 20 (↑ 12 to ↑ 29)
NA=not available

Table 11 Drug Interactions: Changes in Pharmacokinetic Parameters for Tenofovir in the Presence of the Coadministered Drugs
Coadministered Drug | Dose of Coadministered Drug (mg) | TDF Dose (mg) [Subjects received VIREAD 300 mg daily.] | N [N=maximum number of subjects for Cmax, AUC, or Cmin] | Mean % Change of Tenofovir Pharmacokinetic Parameters [Increase = ↑; Decrease = ↓; No Effect = ↔] (90% CI)
Coadministered Drug | Dose of Coadministered Drug (mg) | TDF Dose (mg) [Subjects received VIREAD 300 mg daily.] | N [N=maximum number of subjects for Cmax, AUC, or Cmin] | Cmax | AUC | Cmin
Entecavir | 1 once daily × 10 days | 300 once daily |  | ↔ | ↔ | ↔
Emtricitabine | 200 once daily × 7 days | 300 once daily × 7 days | 17 | ↔ | ↔ | ↔
Ledipasvir/ Sofosbuvir | 90/400 once daily × 10 days | 300 once daily [Study conducted with COMPLERA coadministered with HARVONI.] | 14 | ↑ 32 (↑ 25 to ↑ 39) | ↑ 40 (↑ 31 to ↑ 50) | ↑ 91 (↑ 74 to ↑ 110)
Sofosbuvir/ Velpatasvir | 400/100 once daily | 300 once daily | 24 | ↑ 44 (↑ 33 to ↑ 55) | ↑ 40 (↑ 34 to ↑ 46) | ↑ 84 (↑ 76 to ↑ 92)
Tacrolimus | 0.05 mg/kg twice daily × 7 days | 300 once daily [Study conducted with COMPLERA coadministered with EPCLUSA.] | 21 | ↑ 13 (↑ 1 to ↑ 27) | ↔ | ↔
NA=not available

Table 12 Drug Interactions: Changes in Pharmacokinetic Parameters for Coadministered Drugs in the Presence of RPV
Coadministered Drug | Dose of Coadministered Drug (mg) | RPV Dose (mg) | N [N=maximum number of subjects for Cmax, AUC, or Cmin] | Mean % Change of Coadministered Drug Pharmacokinetic Parameters [Increase = ↑; Decrease = ↓; No Effect = ↔] (90% CI)
Coadministered Drug | Dose of Coadministered Drug (mg) | RPV Dose (mg) | N [N=maximum number of subjects for Cmax, AUC, or Cmin] | Cmax | AUC | Cmin
Acetaminophen | 500 single dose | 150 once daily [The Interaction study has been performed with a dose higher than the recommended dose for RPV (25 mg once daily).] | 16 | ↓ 3 (↓ 14 to ↑ 10) | ↓ 8 (↓ 15 to ↓ 1) | NA
Atorvastatin | 40 once daily | 150 once daily | 16 | ↑ 35 (↑ 8 to ↑ 68) | ↑ 4 (↓ 3 to ↑ 12) | ↓ 15 (↓ 31 to ↑ 3)
2-hydroxy-atorvastatin | 40 once daily | 150 once daily | 16 | ↑ 58 (↑ 33 to ↑ 87) | ↑ 39 (↑ 29 to ↑ 50) | ↑ 32 (↑ 10 to ↑ 58)
4-hydroxy-atorvastatin | 40 once daily | 150 once daily | 16 | ↑ 28 (↑ 15 to ↑ 43) | ↑ 23 (↑ 13 to ↑ 33) | NA
Chlorzoxazone | 500 single dose taken 2 hours after RPV | 150 once daily | 16 | ↓ 2 (↓ 15 to ↑ 13) | ↑ 3 (↓ 5 to ↑ 13) | NA
Digoxin | 0.5 single dose | 25 once daily | 22 | ↑ 6 (↓ 3 to ↑ 17) | ↓ 2 (↓ 7 to ↑ 4) | NA
Ethinyl estradiol | 0.035 once daily | 25 once daily | 17 | ↑ 17 (↑ 6 to ↑ 30) | ↑ 14 (↑ 10 to ↑ 19) | ↑ 9 (↑ 3 to ↑ 16)
Norethindrone | 1 mg once daily | 25 once daily | 17 | ↓ 6 (↓ 17 to ↑ 6) | ↓ 11 (↓ 16 to ↓ 6) | ↓ 1 (↓ 10 to ↑ 8)
Ketoconazole | 400 once daily | 150 once daily | 14 | ↓ 15 (↓ 20 to ↓ 10) | ↓ 24 (↓ 30 to ↓ 18) | ↓ 66 (↓ 75 to ↓ 54)
Ledipasvir | 90 once daily | 25 once daily | 41 | ↑ 1 (↓ 3 to ↑ 5) | ↑ 2 (↓ 3 to ↑ 6) | ↑ 2 (↓ 2 to ↑ 7)
R(-) methadone | 60−100 once daily individualized dose | 25 once daily | 13 | ↓ 14 (↓ 22 to ↓ 5) | ↓ 16 (↓ 26 to ↓ 5) | ↓ 22 (↓ 33 to ↓ 9)
S(+) methadone | 60−100 once daily individualized dose | 25 once daily | 13 | ↓ 13 (↓ 22 to ↓ 3) | ↓ 16 (↓ 26 to ↓ 4) | ↓ 21 (↓ 33 to ↓ 8)
Metformin | 850 single dose | 25 once daily | 20 | ↑ 2 (↓ 5 to ↑ 10) | ↓ 3 (↓ 10 to ↑ 6) | NA
Omeprazole | 20 once daily | 150 once daily | 15 | ↓ 14 (↓ 32 to ↑ 9) | ↓ 14 (↓ 24 to ↓ 3) | NA
Rifampin | 600 once daily | 150 once daily | 16 | ↑ 2 (↓ 7 to ↑ 12) | ↓ 1 (↓ 8 to ↑ 7) | NA
25-desacetylrifampin | 600 once daily | 150 once daily | 16 | ↔ (↓ 13 to ↑ 15) | ↓ 9 (↓ 23 to ↑ 7) | NA
Simeprevir | 150 once daily | 25 once daily | 21 | ↑ 10 (↓ 3 to ↑ 26) | ↑ 6 (↓ 6 to ↑ 19) | ↓ 4 (↓ 17 to ↑ 11)
Sildenafil | 50 single dose | 75 once daily | 16 | ↓ 7 (↓ 20 to ↑ 8) | ↓ 3 (↓ 13 to ↑ 8) | NA
N-desmethyl-sildenafil | 50 single dose | 75 once daily | 16 | ↓ 10 (↓ 20 to ↑ 2) | ↓ 8 (↓ 15 to ↓ 1) | NA
Sofosbuvir | 400 once daily | 25 once daily | 24 | ↑ 9 (↓ 5 to ↑ 25) | ↑ 16 (↑ 10 to ↑ 24) | NA
GS-331007 [The predominant circulating nucleoside metabolite of sofosbuvir.] | 400 once daily | 25 once daily | 24 | ↓ 4 (↓ 10 to ↑ 1) | ↑ 4 (0 to ↑ 7) | ↑ 12 (↑ 7 to ↑ 17)
Velpatasvir | 100 once daily | 25 once daily | 24 | ↓ 4 (↓ 15 to ↑ 10) | ↓ 1 (↓ 12 to ↑ 11) | ↑ 2 (↓ 9 to ↑ 15)
Sofosbuvir | 400 once daily | 25 once daily [Study conducted with ODEFSEY.] | 30 | ↓ 5 (↓ 14 to ↑ 5) | ↑ 1 (↓ 3 to ↑ 6) | NA
GS-331007 | 400 once daily | 25 once daily [Study conducted with ODEFSEY.] | 30 | ↑ 2 (↓ 2 to ↑ 6) | ↑ 4 (↑ 1 to ↑ 6) | NA
Velpatasvir | 100 once daily | 25 once daily | 30 | ↑ 5 (↓ 4 to ↑ 16) | ↑ 1 (↓ 6 to ↑ 7) | ↑ 1 (↓ 5 to ↑ 9)
Voxilaprevir | 100 + 100 once daily | 25 once daily | 30 | ↓ 4 (↓ 16 to ↑ 11) | ↓ 6 (↓ 16 to ↑ 5) | ↑ 2 (↓ 8 to ↑ 12)
TDF | 300 once daily | 150 once daily | 16 | ↑ 19 (↑ 6 to ↑ 34) | ↑ 23 (↑ 16 to ↑ 31) | ↑ 24 (↑ 10 to ↑ 38)
NA = not available

Table 13 Drug Interactions: Changes in Pharmacokinetic Parameters for Coadministered Drugs in the Presence of FTC
Coadministered Drug | Dose of Coadministered Drug (mg) | FTC Dose (mg) | N [All interaction trials conducted in healthy volunteers] | Mean % Change of Coadministered Drug Pharmacokinetic Parameters [No Effect = ↔] (90% CI)
Coadministered Drug | Dose of Coadministered Drug (mg) | FTC Dose (mg) | N [All interaction trials conducted in healthy volunteers] | Cmax | AUC | Cmin
Famciclovir | 500 × 1 | 200 × 1 | 12 | ↔ | ↔ | NA
TDF | 300 once daily × 7 days | 200 once daily × 7 days | 17 | ↔ | ↔ | ↔
NA=not available

No clinically significant drug interactions have been observed between FTC and indinavir, sofosbuvir/velpatasvir, sofosbuvir/velpatasvir/voxilaprevir, stavudine, and zidovudine.

Table 14 Drug Interactions: Changes in Pharmacokinetic Parameters for Coadministered Drugs in the Presence of TDF
Coadministered Drug | Dose of Coadministered Drug (mg) | TDF Dose (mg) | N [All interaction trials conducted in healthy volunteers] | Mean % Change of Coadministered Drug Pharmacokinetic Parameters [Increase = ↑; No Effect = ↔] (90% CI)
Coadministered Drug | Dose of Coadministered Drug (mg) | TDF Dose (mg) | N [All interaction trials conducted in healthy volunteers] | Cmax | AUC | Cmin
Emtricitabine | 200 once daily × 7 days | 300 once daily × 7 days | 17 | ↔ | ↔ | ↑ 20 (↑ 12 to ↑ 29)
Entecavir | 1 once daily × 10 days | 300 once daily | 28 | ↔ | ↑ 13 (↑ 11 to ↑ 15) | ↔
Tacrolimus | 0.05 mg/kg twice daily × 7 days | 300 once daily | 21 | ↔ | ↔ | ↔
NA=not available

No effect on the pharmacokinetic parameters of the following coadministered drugs was observed with TDF: methadone, oral contraceptives (ethinyl estradiol/norgestimate), or ribavirin.

12.4 Microbiology

Mechanism of Action

Emtricitabine: FTC, a synthetic nucleoside analog of cytidine, is phosphorylated by cellular enzymes to form emtricitabine 5'-triphosphate. Emtricitabine 5'-triphosphate inhibits the activity of the HIV-1 RT by competing with the natural substrate deoxycytidine 5'-triphosphate and by being incorporated into nascent viral DNA, which results in chain termination. Emtricitabine 5′-triphosphate is a weak inhibitor of mammalian DNA polymerases α, β, ε, and mitochondrial DNA polymerase γ.

Rilpivirine: RPV is a diarylpyrimidine non-nucleoside reverse transcriptase inhibitor of HIV-1 and inhibits HIV-1 replication by non-competitive inhibition of HIV-1 RT. RPV does not inhibit the human cellular DNA polymerases α, β, and mitochondrial DNA polymerase γ.

Tenofovir DF: TDF is an acyclic nucleoside phosphonate diester analog of adenosine monophosphate. TDF requires initial diester hydrolysis for conversion to tenofovir and subsequent phosphorylations by cellular enzymes to form tenofovir diphosphate. Tenofovir diphosphate inhibits the activity of HIV-1 RT by competing with the natural substrate deoxyadenosine 5′-triphosphate and, after incorporation into DNA, by DNA chain termination. Tenofovir diphosphate is a weak inhibitor of mammalian DNA polymerases α, β, and mitochondrial DNA polymerase γ.

Antiviral Activity

Emtricitabine, Rilpivirine, and TDF: The triple combination of FTC, RPV, and TDF was not antagonistic in cell culture.

Emtricitabine: The antiviral activity of FTC against laboratory and clinical isolates of HIV-1 was assessed in lymphoblastoid cell lines, the MAGI-CCR5 cell line, and peripheral blood mononuclear cells. The 50% effective concentration (EC50) values for FTC were in the range of 0.0013–0.64 µM. FTC displayed antiviral activity in cell culture against HIV-1 clades A, B, C, D, E, F, and G (EC50 values ranged from 0.007–0.075 µM) and showed strain specific activity against HIV-2 (EC50 values ranged from 0.007–1.5 µM). In drug combination studies of FTC with nucleoside reverse transcriptase inhibitors (abacavir, lamivudine, stavudine, tenofovir, zidovudine), non-nucleoside reverse transcriptase inhibitors (delavirdine, EFV, nevirapine, and RPV), and protease inhibitors (amprenavir, nelfinavir, ritonavir, saquinavir), no antagonistic effects were observed.

Rilpivirine: RPV exhibited activity against laboratory strains of wild-type HIV-1 in an acutely infected T-cell line with a median EC50 value for HIV-1IIIB of 0.73 nM. RPV demonstrated limited activity in cell culture against HIV-2 with a median EC50 value of 5220 nM (range 2510–10,830 nM). RPV demonstrated antiviral activity against a broad panel of HIV-1 group M (subtype A, B, C, D, F, G, H) primary isolates with EC50 values ranging from 0.07–1.01 nM and was less active against group O primary isolates with EC50 values ranging from 2.88–8.45 nM. The antiviral activity of RPV was not antagonistic when combined with the NNRTIs EFV, etravirine, or nevirapine; the N(t)RTIs abacavir, didanosine, FTC, lamivudine, stavudine, tenofovir, or zidovudine; the PIs amprenavir, atazanavir, darunavir, indinavir, lopinavir, nelfinavir, ritonavir, saquinavir, or tipranavir; the gp41 fusion inhibitor enfuvirtide; the CCR5 co-receptor antagonist maraviroc; or the integrase strand transfer inhibitor raltegravir.

Tenofovir DF: The antiviral activity of tenofovir against laboratory and clinical isolates of HIV-1 was assessed in lymphoblastoid cell lines, primary monocyte/macrophage cells, and peripheral blood lymphocytes. The EC50 values for tenofovir were in the range of 0.04–8.5 µM. Tenofovir displayed antiviral activity in cell culture against HIV-1 clades A, B, C, D, E, F, G, and O (EC50 values ranged from 0.5–2.2 µM) and showed strain specific activity against HIV-2 (EC50 values ranged from 1.6–5.5 µM). In drug combination studies of tenofovir with NRTIs (abacavir, didanosine, FTC, lamivudine, stavudine, and zidovudine), NNRTIs (delavirdine, EFV, nevirapine, and RPV), and PIs (amprenavir, indinavir, nelfinavir, ritonavir, saquinavir), no antagonistic effects were observed.

Resistance

In Cell Culture

Emtricitabine and Tenofovir DF: HIV-1 isolates with reduced susceptibility to FTC or tenofovir have been selected in cell culture. Reduced susceptibility to FTC was associated with M184V/I substitutions in HIV-1 RT. HIV-1 isolates selected by tenofovir expressed a K65R substitution in HIV-1 RT and showed a 2–4 fold reduction in susceptibility to tenofovir. In addition, a K70E substitution in HIV-1 RT has been selected by tenofovir and results in low-level reduced susceptibility to abacavir, FTC, lamivudine, and tenofovir.

Rilpivirine: RPV-resistant strains were selected in cell culture starting from wild-type HIV-1 of different origins and subtypes as well as NNRTI-resistant HIV-1. The frequently observed amino acid substitutions that emerged and conferred decreased phenotypic susceptibility to RPV included: L100I, K101E, V106I and A, V108I, E138K and G, Q, R, V179F and I, Y181C and I, V189I, G190E, H221Y, F227C, and M230I and L.

In HIV-1-Infected Adult Subjects With No Antiretroviral Treatment History

In the Week 96 pooled resistance analysis for adult subjects receiving RPV or EFV in combination with FTC/TDF in the Phase 3 clinical trials C209 and C215, the emergence of resistance was greater among subjects' viruses in the RPV + FTC/TDF arm compared to the EFV + FTC/TDF arm and was dependent on baseline viral load. In the pooled resistance analysis, 61% (47/77) of the subjects who qualified for resistance analysis (resistance analysis subjects) in the RPV + FTC/TDF arm had virus with genotypic and/or phenotypic resistance to RPV compared to 42% (18/43) of the resistance analysis subjects in the EFV + FTC/TDF arm who had genotypic and/or phenotypic resistance to EFV. Moreover, genotypic and/or phenotypic resistance to FTC or tenofovir emerged in viruses from 57% (44/77) of the resistance analysis subjects in the RPV arm compared to 26% (11/43) in the EFV arm.

Emerging NNRTI substitutions in the RPV resistance analysis of subjects' viruses included V90I, K101E/P/T, E138K/A/Q/G, V179I/L, Y181C/I, V189I, H221Y, F227C/L, and M230L, which were associated with an RPV phenotypic fold change range of 2.6–621. The E138K substitution emerged most frequently during RPV treatment, commonly in combination with the M184I substitution. The FTC and lamivudine resistance-associated substitutions M184I or V and NRTI resistance-associated substitutions (K65R/N, A62V, D67N/G, K70E, Y115F, K219E/R) emerged more frequently in the RPV resistance analysis subjects than in EFV resistance analysis subjects (See Table 15).

NNRTI- and NRTI-resistance substitutions emerged less frequently in the resistance analysis of viruses from subjects with baseline viral loads of ≤100,000 copies/mL compared to viruses from subjects with baseline viral loads of >100,000 copies/mL: 23% (10/44) compared to 77% (34/44) of NNRTI-resistance substitutions and 20% (9/44) compared to 80% (35/44) of NRTI-resistance substitutions. This difference was also observed for the individual FTC/lamivudine and tenofovir resistance substitutions: 22% (9/41) compared to 78% (32/41) for M184I/V and 0% (0/8) compared to 100% (8/8) for K65R/N. Additionally, NNRTI and/or NRTI-resistance substitutions emerged less frequently in the resistance analysis of the viruses from subjects with baseline CD4+ cell counts ≥200 cells/mm^3 compared to the viruses from subjects with baseline CD4+ cell counts <200 cells/mm^3: 32% (14/44) compared to 68% (30/44) of NNRTI-resistance substitutions and 27% (12/44) compared to 73% (32/44) of NRTI-resistance substitutions.

Table 15 Proportion of Frequently Emerging Reverse Transcriptase Substitutions in the HIV-1 Virus of Resistance Analysis Adult Subjects [Subjects who qualified for resistance analysis] Who Received RPV or EFV in Combination with FTC/TDF from Pooled Phase 3 TMC278-C209 and TMC278-C215 Trials in the Week 96 Analysis
 | C209 and C215 N=1096
 | RPV+ FTC/TDF | EFV+ FTC/TDF
 | N=550 | N=546
Subjects who Qualified for Resistance Analysis | 14% (77/550) | 8% (43/546)
Subjects with Evaluable Postbaseline Resistance Data | 70 | 31
Emergent NNRTI Substitutions [V90, L100, K101, K103, V106, V108, E138, V179, Y181, Y188, V189, G190, H221, P225, F227, and M230]
Any | 63% (44/70) | 55% (17/31)
V90I | 14% (10/70) | 0
K101E/P/T/Q | 19% (13/70) | 10% (3/31)
K103N | 1% (1/70) | 39% (12/31)
E138K/A/Q/G | 40% (28/70) | 0
E138K+M184I [This combination of NRTI and NNRTI substitutions is a subset of those with the E138K.] | 30% (21/70) | 0
V179I/D | 6% (4/70) | 10% (3/31)
Y181C/I/S | 13% (9/70) | 3% (1/31)
V189I | 9% (6/70) | 0
H221Y | 10% (7/70) | 0
Emergent NRTI Substitutions [A62V, K65R/N, D67N/G, K70E, L74I, Y115F, M184V/I, L210F, K219E/R]
Any | 63% (44/70) | 32% (10/31)
M184I/V | 59% (41/70) | 26% (8/31)
K65R/N | 11% (8/70) | 6% (2/31)
A62V, D67N/G, K70E, Y115F, or K219E/R [These substitutions emerged in addition to the primary substitutions M184V/I or K65R; A62V (n=2), D67N/G (n=3), K70E (n=4), Y115F (n=2), K219E/R (n=8) in RPV resistance analysis subjects.] | 20% (14/70) | 3% (1/31)

In Virologically Suppressed HIV-1-Infected Adult Subjects

Study 106: Through Week 48, 4 subjects who switched to COMPLERA (4 of 469 subjects, 0.9%) and 1 subject who maintained their ritonavir-boosted protease inhibitor-based regimen (1 of 159 subjects, 0.6%) developed genotypic and/or phenotypic resistance to a study drug. All 4 of the subjects who had resistance emergence on COMPLERA had evidence of FTC resistance and 3 of the subjects had evidence of RPV resistance.

Cross Resistance

Rilpivirine, Emtricitabine, and Tenofovir DF:

In Cell Culture

No significant cross-resistance has been demonstrated between RPV-resistant HIV-1 variants and FTC or tenofovir, or between FTC- or tenofovir-resistant variants and RPV.

Rilpivirine:

Site-Directed NNRTI Mutant Virus

Cross-resistance has been observed among NNRTIs. The single NNRTI substitutions K101P, Y181I, and Y181V conferred 52-fold, 15-fold, and 12-fold decreased susceptibility to RPV, respectively. The combination of E138K and M184I showed 6.7-fold reduced susceptibility to RPV compared to 2.8-fold for E138K alone. The K103N substitution did not show reduced susceptibility to RPV by itself. However, the combination of K103N and L100I resulted in a 7-fold reduced susceptibility to RPV. In another study, the Y188L substitution resulted in a reduced susceptibility to RPV of 9-fold for clinical isolates and 6-fold for site-directed mutants. Combinations of 2 or 3 NNRTI resistance-associated substitutions gave decreased susceptibility to RPV (fold change range of 3.7–554) in 38% and 66% of mutants, respectively.

In HIV-1-Infected Adult Subjects With No Antiretroviral Treatment History

Considering all available cell culture and clinical data, any of the following amino acid substitutions, when present at baseline, are likely to decrease the antiviral activity of RPV: K101E, K101P, E138A, E138G, E138K, E138R, E138Q, V179L, Y181C, Y181I, Y181V, Y188L, H221Y, F227C, M230I, M230L, and the combination of L100I+K103N.

Cross-resistance to EFV, etravirine, and/or nevirapine is likely after virologic failure and development of RPV resistance. In a pooled 96-week analysis for adult subjects receiving RPV in combination with FTC/TDF in the Phase 3 clinical trials TMC278-C209 and TMC278-C215, 43 of the 70 (61%) RPV resistance analysis subjects with postbaseline resistance data had virus with decreased susceptibility to RPV (≥2.5 fold change). Of these, 84% (n=36/43) were resistant to EFV (≥3.3-fold change), 88% (n=38/43) were resistant to etravirine (≥3.2-fold change), and 60% (n=26/43) were resistant to nevirapine (≥6-fold change). In the EFV arm, 3 of the 15 (20%) EFV resistance analysis subjects had viruses with resistance to etravirine and RPV, and 93% (14/15) had resistance to nevirapine. Virus from subjects experiencing virologic failure on RPV in combination with FTC/TDF developed more NNRTI resistance-associated substitutions conferring more cross-resistance to the NNRTI class and had a higher likelihood of cross-resistance to all NNRTIs in the class than subjects who failed on EFV.

Emtricitabine: FTC-resistant isolates (M184V/I) were cross-resistant to lamivudine but retained susceptibility in cell culture to didanosine, stavudine, tenofovir, zidovudine, and NNRTIs (delavirdine, EFV, nevirapine, and RPV). HIV-1 isolates containing the K65R substitution, selected in vivo by abacavir, didanosine, and tenofovir, demonstrated reduced susceptibility to inhibition by FTC. Viruses harboring substitutions conferring reduced susceptibility to stavudine and zidovudine (M41L, D67N, K70R, L210W, T215Y/F, K219Q/E), or didanosine (L74V), remained sensitive to FTC. HIV-1 containing the substitutions associated with NNRTI resistance K103N or RPV-associated substitutions were susceptible to FTC.

Tenofovir DF: The K65R and K70E substitutions selected by tenofovir are also selected in some HIV-1-infected patients treated with abacavir or didanosine. HIV-1 isolates with the K65R and K70E substitutions also showed reduced susceptibility to FTC and lamivudine. Therefore, cross-resistance among these NRTIs may occur in patients whose virus harbors the K65R substitution. HIV-1 isolates from patients (N=20) whose HIV-1 expressed a mean of 3 zidovudine-associated RT amino acid substitutions (M41L, D67N, K70R, L210W, T215Y/F, or K219Q/E/N) showed a 3.1-fold decrease in the susceptibility to tenofovir.

Subjects whose virus expressed an L74V substitution without zidovudine resistance-associated substitutions (N=8) had reduced response to TDF. Limited data are available for patients whose virus expressed a Y115F substitution (N=3), Q151M substitution (N=2), or T69 insertion (N=4), all of whom had a reduced response. HIV-1 containing the substitutions associated with NNRTI resistance K103N and Y181C, or RPV-associated substitutions, were susceptible to tenofovir.

13 NONCLINICAL TOXICOLOGY

13.1 Carcinogenesis, Mutagenesis, Impairment of Fertility

Emtricitabine: In long-term carcinogenicity studies of FTC, no drug-related increases in tumor incidence were found in mice at doses up to 750 mg per kg per day (26 times the human systemic exposure at the therapeutic dose of 200 mg per day) or in rats at doses up to 600 mg per kg per day (31 times the human systemic exposure at the therapeutic dose).

FTC was not genotoxic in the reverse mutation bacterial test (Ames test), or the mouse lymphoma or mouse micronucleus assays.

FTC did not affect fertility in male rats at approximately 140-fold or in male and female mice at approximately 60-fold higher exposures (AUC) than in humans given the recommended 200 mg daily dose. Fertility was normal in the offspring of mice exposed daily from before birth (in utero) through sexual maturity at daily exposures (AUC) of approximately 60-fold higher than human exposures at the recommended 200 mg daily dose.

Rilpivirine: RPV was evaluated for carcinogenic potential by oral gavage administration to mice and rats up to 104 weeks. Daily doses of 20, 60, and 160 mg per kg per day were administered to mice and doses of 40, 200, 500, and 1500 mg per kg per day were administered to rats. In rats, there were no drug-related neoplasms. In mice, RPV was positive for hepatocellular neoplasms in both males and females. The observed hepatocellular findings in mice may be rodent-specific. At the lowest tested doses in the carcinogenicity studies, the systemic exposures (based on AUC) to RPV were 21 fold (mice) and 3 fold (rats), relative to those observed in humans at the recommended dose (25 mg once daily).

RPV has tested negative in the absence and presence of a metabolic activation system, in the in vitro Ames reverse mutation assay and in vitro clastogenicity mouse lymphoma assay. RPV did not induce chromosomal damage in the in vivo micronucleus test in mice.

In a study conducted in rats, there were no effects on mating or fertility with RPV up to 400 mg per kg per day, a dose of RPV that showed maternal toxicity. This dose is associated with an exposure that is approximately 40 times higher than the exposure in humans at the recommended dose of 25 mg once daily.

Tenofovir DF: Long-term oral carcinogenicity studies of TDF in mice and rats were carried out at exposures up to approximately 16 times (mice) and 5 times (rats) those observed in humans at the therapeutic dose for HIV-1 infection. At the high dose in female mice, liver adenomas were increased at exposures 16 times that in humans. In rats, the study was negative for carcinogenic findings at exposures up to 5 times that observed in humans at the therapeutic dose.

Tenofovir DF was mutagenic in the in vitro mouse lymphoma assay and negative in an in vitro bacterial mutagenicity test (Ames test). In an in vivo mouse micronucleus assay, TDF was negative when administered to male mice.

There were no effects on fertility, mating performance, or early embryonic development when TDF was administered to male rats at a dose equivalent to 10 times the human dose based on body surface area comparisons for 28 days prior to mating and to female rats for 15 days prior to mating through day 7 of gestation. There was, however, an alteration of the estrous cycle in female rats.

13.2 Animal Toxicology and/or Pharmacology

Tenofovir DF: Tenofovir and TDF administered in toxicology studies to rats, dogs, and monkeys at exposures (based on AUCs) greater than or equal to 6-fold those observed in humans caused bone toxicity. In monkeys the bone toxicity was diagnosed as osteomalacia. Osteomalacia observed in monkeys appeared to be reversible upon dose reduction or discontinuation of tenofovir. In rats and dogs, the bone toxicity manifested as reduced bone mineral density. The mechanism(s) underlying bone toxicity is unknown.

Evidence of renal toxicity was noted in 4 animal species. Increases in serum creatinine, BUN, glycosuria, proteinuria, phosphaturia, and/or calciuria and decreases in serum phosphate were observed to varying degrees in these animals. These toxicities were noted at exposures (based on AUCs) 2–20 times higher than those observed in humans. The relationship of the renal abnormalities, particularly the phosphaturia, to the bone toxicity is not known.

14 CLINICAL STUDIES

14.1 Adult Subjects

In HIV-1-Infected Adult Subjects With No Antiretroviral Treatment History

The efficacy of COMPLERA is based on the analyses of 48- and 96-week data from two randomized, double-blind, controlled studies (Study C209 [ECHO] and TRUVADA subset of Study C215 [THRIVE]) in treatment-naïve, HIV-1-infected subjects (N=1368). The studies are identical in design with the exception of the background regimen (BR). Subjects were randomized in a 1:1 ratio to receive either RPV 25 mg (N=686) once daily or EFV 600 mg (N=682) once daily in addition to a BR. In Study C209 (N=690), the BR was FTC/TDF. In Study C215 (N=678), the BR consisted of 2 NRTIs: FTC/TDF (60%, n=406), lamivudine/zidovudine (30%, n=204), or abacavir + lamivudine (10%, n=68).

For subjects who received FTC/TDF (N=1096) in studies C209 and C215, the mean age was 37 years (range 18–78), 78% were male, 62% were White, 24% were Black, and 11% were Asian. The mean baseline CD4+ cell count was 265 cells/mm^3 (range 1–888) and 31% had CD4+ cell counts <200 cells/mm^3. The median baseline plasma HIV-1 RNA was 5 log10 copies/mL (range 2–7). Subjects were stratified by baseline HIV-1 RNA. Fifty percent of subjects had baseline viral load ≤100,000 copies/mL, 39% of subjects had baseline viral load between 100,000 copies/mL to 500,000 copies/mL, and 11% of subjects had baseline viral load >500,000 copies/mL.

Treatment outcomes through 96 weeks for the subset of subjects receiving FTC/TDF in studies C209 and C215 (Table 16) are generally consistent with treatment outcomes for all participating subjects (presented in the prescribing information for Edurant). The incidence of virologic failure was higher in the RPV arm than the EFV arm at Week 96. Virologic failures and discontinuations due to adverse events mostly occurred in the first 48 weeks of treatment.

Table 16 Pooled Virologic Outcome of Randomized Treatment of Studies C209 and C215 at Week 96 in Adult Subjects With No Antiviral Treatment History in Combination with FTC/TDF) at Week 96 [Analyses were based on the last observed viral load data within the Week 96 window (Week 90–103).]
 | RPV+ FTC/TDF | EFV+ FTC/TDF
 | N=550 | N=546
HIV-1 RNA <50 copies/mL [Predicted difference (95% CI) of response rate is 0.5% (–4.5% to 5.5%) at Week 96.] | 77% | 77%
HIV-1 RNA ≥50 copies/mL [Includes subjects who had ≥50 copies/mL in the Week 96 window, subjects who discontinued early due to lack or loss of efficacy, subjects who discontinued for reasons other than an adverse event, death, or lack or loss of efficacy and at the time of discontinuation had a viral load value of ≥50 copies/mL, and subjects who had a switch in background regimen that was not permitted by the protocol.] | 14% | 8%
No Virologic Data at Week 96 Window Reasons
Discontinued study due to adverse event or death [Includes subjects who discontinued due to an adverse event or death if this resulted in no on-treatment virologic data in the Week 96 window.] | 4% | 9%
Discontinued study for other reasons [Includes subjects who discontinued for reasons other than an adverse event, death, or lack or loss of efficacy, e.g., withdrew consent, loss to follow-up, etc.] and the last available HIV-1 RNA <50 copies/mL (or missing) | 4% | 6%
Missing data during window but on study | <1% | <1%
HIV-1 RNA <50 copies/mL by Baseline HIV-1 RNA (copies/mL)
≤100,000 | 83% | 80%
>100,000 | 71% | 74%
HIV-1 RNA ≥50 copies/mL by Baseline HIV-1 RNA (copies/mL)
≤100,000 | 7% | 5%
>100,000 | 22% | 12%
HIV-1 RNA <50 copies/mL by Baseline CD4+ Cell Count (cells/mm^3)
<200 | 68% | 72%
≥200 | 82% | 79%
HIV-1 RNA ≥50 copies/mL by Baseline CD4+ Cell Count (cells/mm^3)
<200 | 27% | 12%
≥200 | 8% | 7%

Based on the pooled data from studies C209 and C215, the mean CD4+ cell count increase from baseline at Week 96 was 226 cells/mm^3 for RPV + FTC/TDF-treated subjects and 223 cells/mm^3 for EFV + FTC/TDF-treated subjects.

In Virologically Suppressed HIV-1-Infected Adult Subjects

The efficacy and safety of switching from a ritonavir-boosted protease inhibitor in combination with two NRTIs to COMPLERA was evaluated in Study 106, a randomized, open-label study in virologically suppressed HIV-1-infected adults. Subjects had to be on either their first or second antiretroviral regimen with no history of virologic failure, have no current or past history of resistance to any of the three components of COMPLERA, and must have been suppressed (HIV-1 RNA <50 copies/mL) for at least 6 months prior to screening. Subjects were randomized in a 2:1 ratio to either switch to COMPLERA at baseline (COMPLERA arm, N=317), or stay on their baseline antiretroviral regimen for 24 weeks (SBR arm, N=159) and then switch to COMPLERA for an additional 24 weeks (N=52). Subjects had a mean age of 42 years (range 19–73), 88% were male, 77% were White, 17% were Black, and 17% were Hispanic/Latino. The mean baseline CD4+ cell count was 584 cells/mm^3 (range 42–1484). Randomization was stratified by use of TDF and/or lopinavir/ritonavir in the baseline regimen.

Treatment outcomes are presented in Table 17.

Table 17 Virologic Outcomes of Study GS-US-264-0106 in Virologically Suppressed Subjects
 | COMPLERA | Stayed on Baseline Regimen (SBR)
 | Week 48 [Week 48 window is between Day 295 and 378 (inclusive).] | Week 24 [For subjects in the SBR arm who maintained their baseline regimen for 24 weeks and then switched to COMPLERA, the Week 24 window is between Day 127 and first dose day on COMPLERA.]
 | N=317 | N=159
HIV-1 RNA <50 copies/mL [Predicted difference (95% CI) of response rate for switching to COMPLERA at Week 48 compared to staying on baseline regimen at Week 24 (in absence of Week 48 results from the SBR group by study design) is –0.7% (–6.4% to 5.1%).] | 89% (283/317) | 90% (143/159)
HIV-1 RNA ≥50 copies/mL [Includes subjects who had HIV-1 RNA ≥50 copies/mL in the time window, subjects who discontinued early due to lack or loss of efficacy, and subjects who discontinued for reasons other than an adverse event or death and at the time of discontinuation had a viral load value of ≥50 copies/mL.] | 3% (8/317) | 5% (8/159)
No Virologic Data at Week 24 Window
Discontinued study drug due to AE or death [Includes subjects who discontinued due to adverse event or death at any time point from Day 1 through the time window if this resulted in no virologic data on treatment during the specified window.] | 2% (7/317) | 0%
Discontinued study drug due to other reasons and last available HIV-1 RNA <50 copies/mL [Includes subjects who discontinued for reasons other than an adverse event, death, or lack or loss of efficacy, e.g., withdrew consent, loss to follow-up, etc.] | 5% (16/317) | 3% (5/159)
Missing data during window but on study drug | 1% (3/317) | 2% (3/159)

14.2 Pediatric Subjects

The pharmacokinetics, safety, and efficacy of RPV in combination with other antiretroviral agents was evaluated in a single-arm, open-label Phase 2 trial in antiretroviral treatment-naïve HIV-1-infected pediatric subjects 12 to less than 18 years of age and weighing at least 32 kg (TMC-C213). Thirty-six (36) subjects were enrolled with a median age of 14.5 years (range 12 to 17 years), and were 55.6% female, 88.9% Black, and 11.1% Asian. The majority of subjects (24/36) received RPV in combination with FTC and TDF. Of these 24 subjects, 20 had baseline HIV RNA ≤100,000 copies/mL. The baseline characteristics and efficacy outcomes at Week 48 are further described below for the 20 subjects.

The median baseline plasma HIV-1 RNA and CD4+ cell count were 49,550 (range 2060 to 92,600 copies/mL) and 437.5 cells/mm^3 (range 123 to 983 cells/mm^3), respectively. At Week 48, 80% (16/20) of the subjects had HIV RNA <50 copies/mL, 15% (3/20) had HIV RNA ≥50 copies/mL, and one subject discontinued therapy prior to Week 48 and before reaching virologic suppression (HIV RNA <50 copies/mL). At Week 48, the mean increase in CD4+ cell count from baseline was 225 cells/mm^3.

16 HOW SUPPLIED/STORAGE AND HANDLING

COMPLERA tablets are purplish pink, capsule shaped, film coated, debossed with "GSI" on one side, and plain faced on the other side. Each bottle contains 30 tablets (NDC 61958-1101-1), a silica gel desiccant, and a polyester fiber coil, and is closed with a child-resistant closure.

STORAGE AND HANDLING

Store at 25 °C (77 °F), excursions permitted to 15 °C–30 °C (59 °F–86 °F) [See USP Controlled Room Temperature].

Keep container tightly closed.

Dispense only in original container.

17 PATIENT COUNSELING INFORMATION

Advise the patient to read the FDA-approved patient labeling (Patient Information).

Posttreatment Acute Exacerbation of Hepatitis B in Patients Coinfected with HIV-1 and HBV

Severe acute exacerbations of hepatitis B have been reported in patients who are coinfected with HBV and HIV-1 and who have discontinued products containing FTC or TDF [see Warnings and Precautions (5.1)]. Advise patients to not discontinue COMPLERA without first informing their healthcare provider.

Severe Skin Reactions and Hypersensitivity

Advise patients to immediately contact their healthcare provider if they develop a rash. Instruct patients to immediately stop taking COMPLERA and seek medical attention if they develop a rash associated with any of the following symptoms, as it may be a sign of a more serious reaction such as DRESS severe hypersensitivity: fever, blisters, mucosal involvement, eye inflammation (conjunctivitis), severe allergic reaction causing swelling of the face, eyes, lips, mouth, tongue, or throat which may lead to difficulty swallowing or breathing, and any signs and symptoms of liver problems, as they may be a sign of a more serious reaction. Patients should understand that if severe rash occurs, they will be closely monitored, laboratory tests will be performed and appropriate therapy will be initiated [see Warnings and Precautions (5.2)].

Hepatotoxicity

Inform patients that hepatotoxicity has been reported with COMPLERA and that monitoring for hepatotoxicity is recommended [see Warnings and Precautions (5.3)].

Depressive Disorders

Inform patients that depressive disorders (depressed mood, depression, dysphoria, major depression, mood altered, negative thoughts, suicide attempt, suicidal ideation) have been reported with COMPLERA. Advise patients to seek immediate medical evaluation if they experience depressive symptoms [see Warnings and Precautions (5.4)].

New Onset or Worsening Renal Impairment

Inform patients that renal impairment, including cases of acute renal failure and Fanconi syndrome, has been reported in association with the use of TDF. COMPLERA should be avoided with concurrent or recent use of a nephrotoxic agent (e.g., high-dose or multiple NSAIDs) [see Warnings and Precautions (5.5)].

Bone Loss and Mineralization Defects

Inform patients that decreases in bone mineral density have been observed with the use of TDF. Assessment of bone mineral density (BMD) should be considered in patients who have a history of pathologic bone fracture or other risk factors for osteoporosis or bone loss [see Warnings and Precautions (5.6)].

Drug Interactions

COMPLERA may interact with many drugs and is not recommended to be coadministered with numerous drugs. Advise patients to report to their healthcare provider the use of any other prescription or nonprescription medication or herbal products, including St. John's wort [see Contraindications (4), Warnings and Precautions (5.7), and Drug Interactions (7)].

For patients receiving rifabutin, an additional 25 mg tablet of RPV (Edurant) once per day is recommended to be taken concomitantly with COMPLERA and with a meal for the duration of rifabutin coadministration.

Lactic Acidosis and Severe Hepatomegaly

Inform patients that lactic acidosis and severe hepatomegaly with steatosis, including fatal cases, have been reported. Treatment with COMPLERA should be suspended in any patient who develops clinical symptoms suggestive of lactic acidosis or pronounced hepatotoxicity [see Warnings and Precautions (5.8)].

Immune Reconstitution Syndrome

Inform patients to inform their healthcare provider immediately of any signs and symptoms of inflammation from previous infections, which may occur soon after anti-HIV treatment is started [see Warnings and Precautions (5.9)].

Dosing Instructions

Advise patients that it is important to take COMPLERA on a regular dosing schedule with food and to avoid missing doses. A protein drink is not a substitute for food. If the healthcare provider decides to stop COMPLERA and the patient is switched to new medicines to treat HIV that include RPV tablets, the RPV tablets should be taken only with a meal.

Pregnancy Registry

Inform patients that there is an antiretroviral pregnancy registry to monitor fetal outcomes in those exposed to COMPLERA during pregnancy [see Use in Specific Populations (8.1)].

Lactation

Instruct patients with HIV-1 infection not to breastfeed because HIV-1 can be passed to the baby in breast milk [see Use in Specific Populations (8.2)].

Manufactured and distributed by:
Gilead Sciences, Inc.
Foster City, CA 94404

COMPLERA, EMTRIVA, EPCLUSA, GSI, HARVONI, ODEFSEY, TRUVADA, VIREAD, and VOSEVI are trademarks of Gilead Sciences, Inc., or its related companies. All other trademarks referenced herein are the property of their respective owners.

© 2019 Gilead Sciences, Inc. All rights reserved.

202123-GS-013

Patient Information
COMPLERA® (kom-PLEH-rah)
(emtricitabine, rilpivirine, tenofovir disoproxil fumarate)
tablets

Important: Ask your healthcare provider or pharmacist about medicines that should not be taken with COMPLERA. For more information, see the section "What should I tell my healthcare provider before taking COMPLERA?"

What is the most important information I should know about COMPLERA?
COMPLERA can cause serious side effects, including:
Worsening of Hepatitis B virus (HBV) infection. Your healthcare provider will test you for HBV before starting treatment with COMPLERA. If you have HBV infection and take COMPLERA, your HBV may get worse (flare-up) if you stop taking COMPLERA. A "flare-up" is when your HBV infection suddenly returns in a worse way than before.

- Do not stop taking COMPLERA without first talking to your healthcare provider.
- Do not run out of COMPLERA. Refill your prescription or talk to your healthcare provider before your COMPLERA is all gone.
- If you stop taking COMPLERA, your healthcare provider will need to check your health often and do blood tests regularly for several months to check your HBV infection. Tell your healthcare provider about any new or unusual symptoms you may have after you stop taking COMPLERA.

For more information about side effects, see the section "What are the possible side effects of COMPLERA?".

What is COMPLERA?
COMPLERA is a prescription medicine that is used to treat Human Immunodeficiency Virus-1 (HIV-1) in people weighing at least 77 lb (35 kg) who:

- have never taken HIV-1 medicines before, and who have an amount of HIV-1 in their blood (this is called 'viral load') that is no more than 100,000 copies/mL before they start taking COMPLERA,
  or
- in certain people who have a viral load that is less than 50 copies/mL when they start taking COMPLERA, to replace their current HIV-1 medicines.

HIV-1 is the virus that causes AIDS (Acquired Immune Deficiency Syndrome). COMPLERA does not cure HIV-1 or AIDS.
COMPLERA contains 3 medicines (emtricitabine, rilpivirine, tenofovir disoproxil fumarate) combined in one tablet. Emtricitabine (EMTRIVA®) and tenofovir disoproxil fumarate (VIREAD®) are HIV-1 nucleoside analog reverse transcriptase inhibitors (NRTIs). Rilpivirine (Edurant®) is an HIV-1 non-nucleoside analog reverse transcriptase inhibitor (NNRTI).
It is not known if COMPLERA is safe and effective in children less than 12 years of age or who weigh less than 77 lb (35 kg).

Who should not take COMPLERA?
Do not take COMPLERA if you also take:

- anti-seizure medicines:
  - carbamazepine
  - oxcarbazepine
  - phenobarbital
  - phenytoin
- anti-tuberculosis (anti-TB) medicines:
  - rifampin
  - rifapentine
- proton pump inhibitor (PPI) medicine for certain stomach or intestinal problems:
  - dexlansoprazole
  - esomeprazole
  - lansoprazole
  - omeprazole
  - pantoprazole sodium
  - rabeprazole
- more than 1 dose of the steroid medicine dexamethasone or dexamethasone sodium phosphate
- St. John's wort (Hypericum perforatum)

What should I tell my healthcare provider before taking COMPLERA?
Before taking COMPLERA, tell your healthcare provider about all your medical conditions, including if you:

- have liver problems, including hepatitis B or C virus infection
- have kidney problems
- have a history of depression or suicidal thoughts
- have bone problems
- are pregnant or plan to become pregnant. It is not known if COMPLERA can harm your unborn child. Tell your healthcare provider if you become pregnant during treatment with COMPLERA.
  Pregnancy Registry. There is a pregnancy registry for those who take COMPLERA during pregnancy. The purpose of this registry is to collect information about the health of you and your baby. Talk with your healthcare provider about how you can take part in this registry.
- are breastfeeding or plan to breastfeed. Do not breastfeed if you are taking COMPLERA.
  - You should not breastfeed if you have HIV-1 because of the risk of passing HIV-1 to your baby.
  - At least two of the medicines contained in COMPLERA can be passed to your baby in your breast milk.
  - Talk with your healthcare provider about the best way to feed your baby during treatment with COMPLERA.

Tell your healthcare provider about all the medicines you take, including prescription and over-the-counter medicines, vitamins, and herbal supplements.
Some medicines interact with COMPLERA. Keep a list of your medicines to show your healthcare provider and pharmacist when you get a new medicine.

- You can ask your healthcare provider or pharmacist for a list of medicines that can interact with COMPLERA.
- Do not start taking a new medicine without telling your healthcare provider. Your healthcare provider can tell you if it is safe to take COMPLERA with other medicines.

How should I take COMPLERA?

- Take COMPLERA exactly as your healthcare provider tells you to take it.
- Take COMPLERA with food. Taking COMPLERA with food is important to help get the right amount of medicine in your body. A protein drink does not replace food. If your healthcare provider decides to stop COMPLERA and you are switched to new medicines to treat HIV-1 that include rilpivirine tablets, the rilpivirine tablets should be taken only with a meal.
- Do not change your dose or stop taking COMPLERA without first talking with your healthcare provider. Stay under the care of your healthcare provider during treatment with COMPLERA.
- If you miss a dose of COMPLERA within 12 hours of the time you usually take it, take your dose of COMPLERA with food as soon as possible. Then, take your next dose of COMPLERA at the regularly scheduled time. If you miss a dose of COMPLERA by more than 12 hours of the time you usually take it, wait and then take the next dose of COMPLERA at the regularly scheduled time.
- Do not take more than your prescribed dose to make up for a missed dose.
- If you take too much COMPLERA, contact your local poison control center or go to the nearest hospital emergency room right away.
- When your COMPLERA supply starts to run low, get more from your healthcare provider or pharmacy. It is very important not to run out of COMPLERA. The amount of virus in your blood may increase if the medicine is stopped for even a short time.

What are the possible side effects of COMPLERA?
COMPLERA can cause serious side effects, including:

- See "What is the most important information I should know about COMPLERA?"
  Severe skin rash and allergic reactions. Skin rash is a common side effect of COMPLERA. Rash can be serious. Call your healthcare provider right away if you get a rash. In some cases, rash and allergic reaction may need to be treated in a hospital. If you get a rash with any of the following symptoms, stop taking COMPLERA and call your healthcare provider or get medical help right away:

- fever
- skin blisters
- mouth sores
- redness or swelling of the eyes (conjunctivitis)

- swelling of the face, lips, mouth, tongue or throat
- trouble breathing or swallowing
- pain on the right side of the stomach (abdominal) area
- dark or "tea colored" urine

- Severe liver problems. In rare cases, severe liver problems can happen that can lead to death. Tell your healthcare provider right away if you get these symptoms: skin or the white part of your eyes turns yellow, dark "tea-colored" urine, light-colored stools, loss of appetite for several days or longer, nausea, or stomach-area pain.
- Change in liver enzymes. People with a history of hepatitis B or C virus infection or who have certain liver enzyme changes may have an increased risk of developing new or worsening liver problems during treatment with COMPLERA. Liver problems can also happen during treatment with COMPLERA in people without a history of liver disease. Your healthcare provider may need to do tests to check your liver enzymes before and during treatment with COMPLERA.
- Depression or mood changes. Tell your healthcare provider right away if you have any of the following symptoms:
  - feel sad or hopeless
  - feel anxious or restless
  - have thoughts of hurting yourself (suicide) or have tried to hurt yourself
- New or worse kidney problems, including kidney failure, can happen in some people who take COMPLERA. Your healthcare provider should do blood tests to check your kidneys before starting treatment with COMPLERA. If you have had kidney problems in the past or need to take another medicine that can cause kidney problems, your healthcare provider may need to do blood tests to check your kidneys during your treatment with COMPLERA.
- Bone problems can happen in some people who take COMPLERA. Bone problems include bone pain, softening, or thinning (which may lead to fractures). Your healthcare provider may need to do additional tests to check your bones.
- Too much lactic acid in your blood (lactic acidosis). Too much lactic acid is a serious but rare medical emergency that can lead to death. Tell your healthcare provider right away if you get these symptoms: weakness or being more tired than usual, unusual muscle pain, being short of breath or fast breathing, stomach pain with nausea and vomiting, cold or blue hands and feet, feel dizzy or lightheaded, or a fast or abnormal heartbeat.
- Changes in your immune system (Immune Reconstitution Syndrome) can happen when you start taking HIV-1 medicines. Your immune system may get stronger and begin to fight infections that have been hidden in your body for a long time. Tell your healthcare provider right away if you start having new symptoms after starting your HIV-1 medicine.

The most common side effects of rilpivirine, one of the medicines in COMPLERA, include:

- depression
- trouble sleeping
- headache

The most common side effects of emtricitabine and tenofovir disoproxil fumarate, two of the medicines in COMPLERA, include:

- diarrhea
- nausea
- tiredness
- headache
- dizziness

- depression
- trouble sleeping
- abnormal dreams
- rash

These are not all the possible side effects of COMPLERA.
Call your healthcare provider for medical advice about side effects. You may report side effects to FDA at 1-800-FDA-1088.

How should I store COMPLERA?

- Store COMPLERA at room temperature between 68 °F to 77 °F (20 °C to 25 °C).
- Keep COMPLERA in its original container and keep the container tightly closed.
- Do not use COMPLERA if the seal over the bottle opening is broken or missing.

Keep COMPLERA and all other medicines out of reach of children.

General information about safe and effective use of COMPLERA
Medicines are sometimes prescribed for purposes other than those listed in a Patient Information leaflet. Do not use COMPLERA for a condition for which it was not prescribed. Do not give COMPLERA to other people, even if they have the same symptoms you have. It may harm them. You can ask your healthcare provider or pharmacist for information about COMPLERA that is written for health professionals.
For more information, call 1-800-445-3235 or go to www.COMPLERA.com.

What are the ingredients of COMPLERA?
Active ingredients: emtricitabine, rilpivirine hydrochloride, and tenofovir disoproxil fumarate.
Inactive ingredients: croscarmellose sodium, lactose monohydrate, magnesium stearate, microcrystalline cellulose, polysorbate 20 povidone, pregelatinized starch. The tablet film coating contains FD&C Blue #2 aluminum lake, FD&C Yellow #6 aluminum lake, hypromellose, iron oxide red, lactose monohydrate, polyethylene glycol, titanium dioxide, triacetin.
Manufactured and distributed by: Gilead Sciences, Inc. Foster City, CA 94404
COMPLERA, EMTRIVA, and VIREAD are trademarks of Gilead Sciences, Inc., or its related companies. All other trademarks referenced herein are the property of their respective owners.
© 2019 Gilead Sciences, Inc. All rights reserved.
202123-GS-013

This Patient Information has been approved by the U.S. Food and Drug Administration.

Revised: 11/2019

PRINCIPAL DISPLAY PANEL - 30 Tablet Bottle Label

NDC 61958-1101-1
30 tablets

COMPLERA®
(emtricitabine, rilpivirine,
tenofovir disoproxil fumarate)
tablets
200 mg/25 mg/300 mg
Rx only

Note to pharmacist:
Do not cover ALERT box with pharmacy label.

ALERT: Find out about medicines that
should NOT be taken with COMPLERA